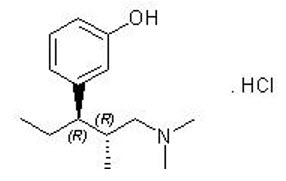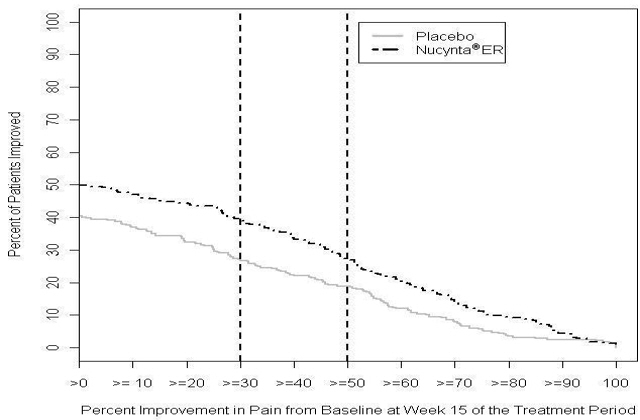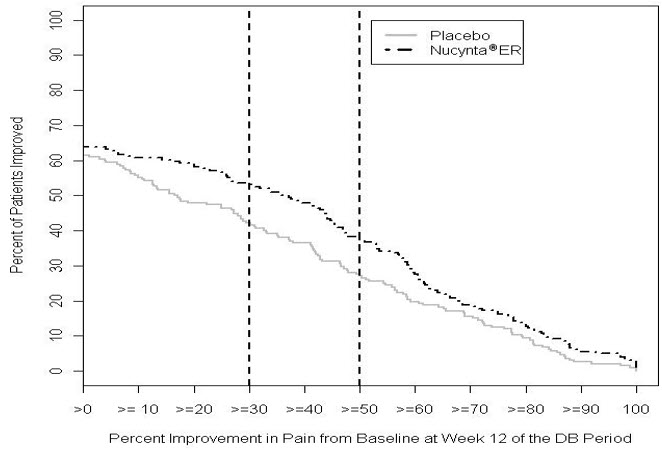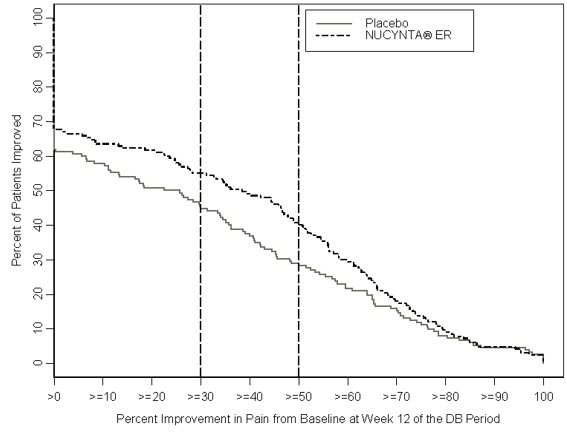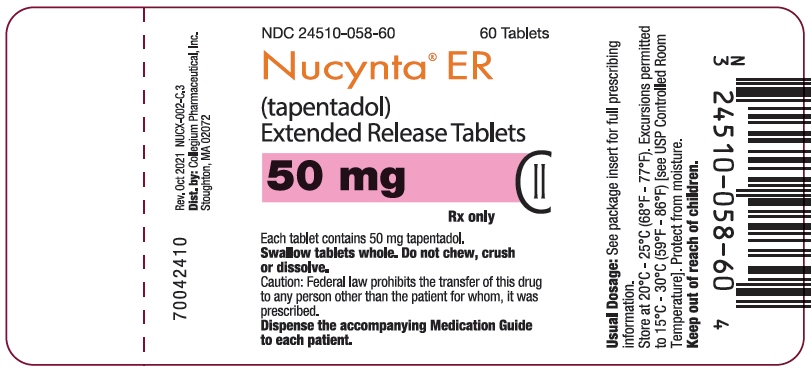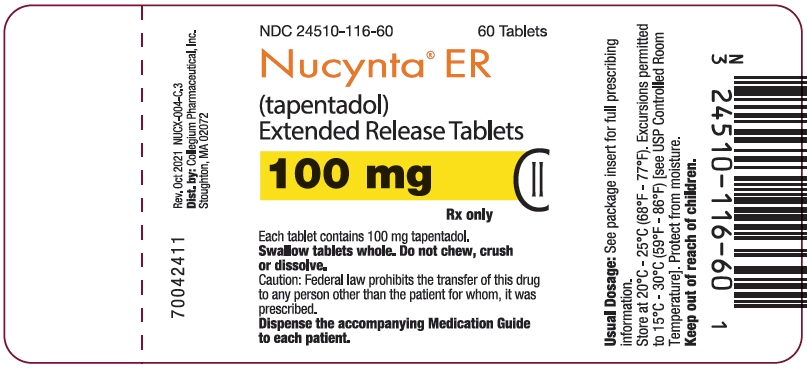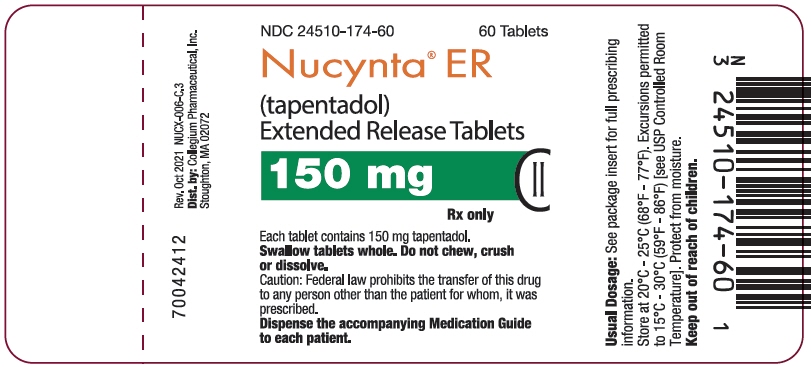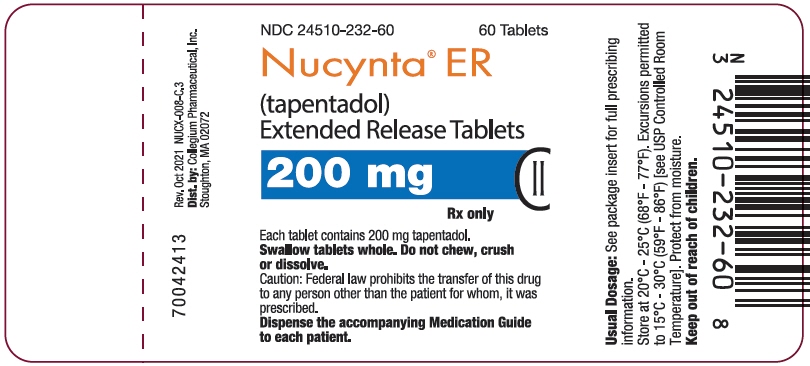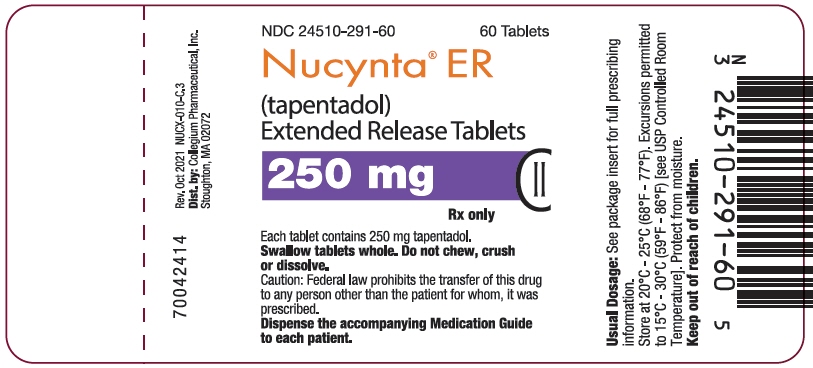 DRUG LABEL: Nucynta
NDC: 24510-058 | Form: TABLET, FILM COATED, EXTENDED RELEASE
Manufacturer: Collegium Pharmaceutical, Inc.
Category: prescription | Type: HUMAN PRESCRIPTION DRUG LABEL
Date: 20251230
DEA Schedule: CII

ACTIVE INGREDIENTS: TAPENTADOL HYDROCHLORIDE 50 mg/1 1
INACTIVE INGREDIENTS: POLYETHYLENE GLYCOL, UNSPECIFIED; HYPROMELLOSE, UNSPECIFIED; .ALPHA.-TOCOPHEROL; POLYVINYL ALCOHOL, UNSPECIFIED; TITANIUM DIOXIDE; TALC; SHELLAC; PROPYLENE GLYCOL; FERROSOFERRIC OXIDE

HIGHLIGHTS OF PRESCRIBING INFORMATION

These highlights do not include all the information needed to use NUCYNTA® ER safely and effectively. See full prescribing information for NUCYNTA® ER
NUCYNTA® ER (tapentadol) extended-release tablets for oral use C-II
Initial U.S. Approval: 2008

WARNING: SERIOUS AND LIFE-THREATENING RISKS FROM USE OF NUCYNTA ER

WARNING: SERIOUS LIFE-THREATENING RISKS FROM USE OF NUCYNTA ER

See FULL PRESCRIBING INFORMATION for complete boxed warning.

- NUCYNTA ER exposes users to risks of addiction, abuse, and misuse, which can lead to overdose and death. Assess each patient's risk before prescribing and reassess regularly for development of these behaviors or conditions. (5.1)
- Serious, life-threatening, or fatal respiratory depression may occur, especially upon initiation or following a dosage increase. To reduce the risk of respiratory depression, proper dosing and titration of NUCYNTA ER are essential. Instruct patients to swallow NUCYNTA ER tablets whole to avoid exposure to a potentially fatal dose of tapentadol. (2.1, 5.2)
- Accidental ingestion of NUCYNTA ER, especially in children, can result in fatal overdose of tapentadol. (5.2)
- Instruct patients not to consume alcohol or any products containing alcohol while taking NUCYNTA ER because co-ingestion can result in fatal plasma tapentadol levels. (5.3)
- Concomitant use of opioids with benzodiazepines or other central nervous system (CNS) depressants, including alcohol, may result in profound sedation, respiratory depression, coma, and death. Reserve concomitant prescribing for use in patients for whom alternative treatment options are inadequate. (5.3, 7)
- Advise pregnant women using opioids for an extended period of time of the risk of Neonatal Opioid Withdrawal Syndrome, which may be life-threatening if not recognized and treated. Ensure that management by neonatology experts will be available at delivery. (5.4)
- Healthcare providers are strongly encouraged to complete a REMS-compliant education program and to counsel patients and caregivers on serious risks, safe use, and the importance of reading the Medication Guide with each prescription. (5.5)

RECENT MAJOR CHANGES

Boxed Warning | 12/2025
Indications and Usage (1) | 12/2025
Dosage and Administration (2.1, 2.3, 2.6) | 12/2025
Warnings and Precautions (5.1, 5.2, 5.3, 5.12, 5.14) | 12/2025

1 INDICATIONS AND USAGE

NUCYNTA ER is an opioid agonist indicated for the management of:

- severe and persistent pain in adults that requires an opioid analgesic and that cannot be adequately treated with alternative options, including immediate-release opioids. (1)
- severe and persistent neuropathic pain associated with diabetic peripheral neuropathy (DPN) in adults that requires opioid analgesic and that cannot be adequately treated with alternative options, including immediate-release opioids. (1)

Limitations of Use

- Because of the risks of addiction, abuse, misuse, overdose, and death, which can occur at any dosage or duration and persist over the course of therapy, reserve opioid analgesics, including NUCYNTA ER, for use in patients for whom alternative treatment options are ineffective, not tolerated, or would be otherwise inadequate to provide sufficient management of pain. (1, 5.1)
- NUCYNTA ER is not indicated as an as-needed (prn) analgesic. (1)

2 DOSAGE AND ADMINISTRATION

- NUCYNTA ER should be prescribed only by healthcare professionals who are knowledgeable about the use of extended-release/long-acting opioids and how to mitigate the associated risks. (2.1)
- Use the lowest effective dosage for the shortest duration of time consistent with individual patient treatment goals. Reserve titration to higher doses of NUCYNTA ER for patients in whom lower doses are insufficiently effective and in whom the expected benefits of using a higher dose opioid clearly outweigh the substantial risks (2.1).
- Initiate the dosing regimen for each patient individually, taking into account the patient's underlying cause and severity of pain, prior analgesic treatment, and response, and risk factors for addiction, abuse, and misuse. (5.1)
- Respiratory depression can occur at any time during opioid therapy, especially when initiating and following dosage increases with NUCYNTA ER. Consider this risk when selecting an initial dose and when making dose adjustments. (2.1, 5.2)
- Discuss opioid overdose reversal agents and options for acquiring them with the patient and/or caregiver, both when initiating and renewing treatment with NUCYNTA ER, especially if the patient has additional risk factors for overdose, or close contacts at risk for exposure and overdose.(2.2, 5.1, 5.2, 5.3)
- NUCYNTA ER is administered orally twice daily (approximately every 12 hours). (2.1)
- Instruct patients to swallow NUCYNTA ER tablets intact, and not to cut, break, chew, crush, or dissolve the tablets (risk of potentially fatal overdose). (2.1, 5.1)
- Instruct patients to take tablets one at a time, with enough water to ensure complete swallowing immediately after placing in mouth.(2.1)
- Do not exceed a total daily dose of NUCYNTA ER of 500 mg. (2.1)
- For patients who are not opioid tolerant, initiate treatment with 50 mg tablet orally twice daily (approximately every 12 hours). See full prescribing information for instructions on conversion, titration, and maintenance of therapy. (2.3, 2.4)
- Titrate patients with dose increases of 50 mg no more than twice daily every three days. (2.4)
- Periodically reassess patients receiving NUCYNTA ER to evaluate the continued need for opioid analgesics to maintain pain control, for the signs or symptoms of adverse reactions, and for the development of addiction, abuse, or misuse. (2.4)
- Moderate Hepatic Impairment: Initiate treatment with 50 mg NUCYNTA ER no more than every 24 hours. Do not exceed 100 mg per day. Regularly evaluate for respiratory and central nervous system depression (2.5)
- Do not rapidly reduce or abruptly discontinue NUCYNTA ER in a physically-dependent patient because rapid reduction or abrupt discontinuation of opioid analgesics has resulted in serious withdrawal symptoms, uncontrolled pain, and suicide. (2.6, 5.14)

3 DOSAGE FORMS AND STRENGTHS

Extended-release tablets: 50 mg, 100 mg, 150 mg, 200 mg, 250 mg (3)

4 CONTRAINDICATIONS

- Significant respiratory depression (4)
- Acute or severe bronchial asthma (4)
- Known or suspected paralytic ileus (4)
- Hypersensitivity to tapentadol or to any other ingredients of the product (4)
- Concurrent use of monoamine oxidase inhibitors (MAOIs) or use of MAOIs within the last 14 days. (4)

5 WARNINGS AND PRECAUTIONS

- Opioid-Induced Hyperalgesia and Allodynia: Opioid-Induced Hyperalgesia (OIH) occurs when an opioid analgesic paradoxically causes an increase in pain, or an increase in sensitivity to pain. If OIH is suspected, carefully consider appropriately decreasing the dose of the current opioid analgesic or opioid rotation. (5.6)
- Serotonin Syndrome with Concomitant Use of Serotonergic Drugs: Potentially life-threatening condition could result from concomitant serotonergic drug administration. Discontinue NUCYNTA ER if serotonin syndrome is suspected. (5.7)
- Life-Threatening Respiratory Depression in Patients with Chronic Pulmonary Disease or in Elderly, Cachectic, or Debilitated Patients: Regularly evaluate, particularly during initiation and titration. (5.8)
- Adrenal Insufficiency: If diagnosed, treat with physiologic replacement of corticosteroids, and wean patient off of the opioid. (5.9)
- Severe Hypotension: Regularly evaluate during dosage initiation and titration. Avoid use of NUCYNTA ER in patients with circulatory shock. (5.10)
- Risks of Use in Patients with Increased Intracranial Pressure, Brain Tumors, Head Injury, or Impaired Consciousness: Monitor for sedation and respiratory depression. Avoid use of NUCYNTA ER in patients with impaired consciousness or coma. (5.11)

6 ADVERSE REACTIONS

The most common (≥10%) adverse reactions were nausea, constipation, dizziness, headache, and somnolence. (6)

To report SUSPECTED ADVERSE REACTIONS, contact Collegium Pharmaceutical, Inc. at 1-855-331-5615 or FDA at 1-800-FDA-1088 or www.fda.gov/medwatch.

7 DRUG INTERACTIONS

- Mixed Agonist/Antagonist and Partial Agonist Opioid Analgesics: Avoid use with NUCYNTA ER because they may reduce analgesic effect of NUCYNTA ER or precipitate withdrawal symptoms. (5.13, 7)

8 USE IN SPECIFIC POPULATIONS

- Pregnancy: Based on animal data, may cause fetal harm. (8.1)
- Lactation: Not recommended. (8.2)
- Severe Hepatic or Renal Impairment: Use not recommended. (8.6, 8.7)

FULL PRESCRIBING INFORMATION

WARNING: SERIOUS AND LIFE-THREATENING RISKS FROM USE OF NUCYNTA ER

Addiction, Abuse, and Misuse

Because the use of NUCYNTA ER exposes patients and other users to the risks of opioid addiction, abuse, and misuse, which can lead to overdose and death assess, each patient's risk prior to prescribing and reassess all patients regularly for the development of these behaviors and conditions [see Warnings and Precautions (5.1)].

Life-Threatening Respiratory Depression

Serious, life-threatening, or fatal respiratory depression may occur with use of NUCYNTA ER, especially during initiation or following a dosage increase. To reduce the risk of respiratory depression, proper dosing and titration of NUCYNTA ER are essential. Instruct patients to swallow NUCYNTA ER tablets whole; crushing, chewing, or dissolving NUCYNTA ER tablets can cause rapid release and absorption of a potentially fatal dose of tapentadol [see Warnings and Precautions (5.2)].

Accidental Ingestion

Accidental ingestion of even one dose of NUCYNTA ER, especially by children, can result in a fatal overdose of tapentadol [see Warnings and Precautions (5.2)].

Interaction with Alcohol

Instruct patients not to consume alcoholic beverages or use prescription or nonprescription products that contain alcohol while taking NUCYNTA ER. The co-ingestion of alcohol with NUCYNTA ER may result in increased plasma tapentadol levels and a potentially fatal overdose of tapentadol [see Warnings and Precautions (5.3)].

Risks From Concomitant Use With Benzodiazepines Or Other CNS Depressants

Concomitant use of opioids with benzodiazepines or other central nervous system (CNS) depressants, including alcohol, may result in profound sedation, respiratory depression, coma, and death. Reserve concomitant prescribing of NUCYNTA ER and benzodiazepines or other CNS depressants for use in patients for whom alternative treatment options are inadequate [see Warnings and Precautions (5.3), Drug Interactions (7)].

Neonatal Opioid Withdrawal Syndrome (NOWS)

Advise pregnant women using opioids for an extended period of time of the risk of Neonatal Opioid Withdrawal Syndrome, which may be life-threatening if not recognized and treated. Ensure that management by neonatology experts will be available at delivery [see Warnings and Precautions (5.4)].

Opioid Analgesic Risk Evaluation and Mitigation Strategy (REMS)

Healthcare providers are strongly encouraged to complete a REMS-compliant education program and to counsel patients and caregivers on serious risks, safe use, and the importance of reading the Medication Guide with each prescription [see Warnings and Precautions (5.5)].

1 INDICATIONS AND USAGE

NUCYNTA ER (tapentadol) is indicated for the management of:

- Severe and persistent pain in adults that requires an opioid analgesic and that cannot be adequately treated with alternative options, including immediate-release opioids.
- Severe and persistent neuropathic pain associated with diabetic peripheral neuropathy (DPN) in adults that requires an opioid analgesic and that cannot be adequately treated with alternative options, including immediate-release opioids.

Limitations of Use

- Because of the risks of addiction, abuse, misuse, overdose, and death, which can occur at any dosage or duration and persist over the course of therapy [see Warnings and Precautions (5.1)], reserve opioid analgesics, including NUCYNTA ER, for use in patients for whom alternative treatment options are ineffective, not tolerated, or would be otherwise inadequate to provide sufficient management of pain.
- NUCYNTA ER is not indicated as an as-needed (prn) analgesic.

2 DOSAGE AND ADMINISTRATION

2.1 Important Dosage and Administration Instructions

- NUCYNTA ER should be prescribed only by healthcare professionals who are knowledgeable about the use of extended-release/long-acting opioids and how to mitigate the associated risks.
- Use the lowest effective dosage for the shortest duration of time consistent with individual patient treatment goals [see Warnings and Precautions (5)]. Because the risk of overdose increases as opioid doses increase, reserve titration to higher doses of NUCYNTA ER for patients in whom lower doses are insufficiently effective and in whom the expected benefits of using a higher dose opioid clearly outweigh the substantial risks.
- Initiate the dosing regimen for each patient individually, taking into account the patient's underlying cause and severity of pain, prior analgesic treatment and response, and risk factors for addiction, abuse, and misuse [see Warnings and Precautions (5.1)]
- Respiratory depression can occur at any time during opioid therapy, especially when initiating and following dosage increases with NUCYNTA ER. Consider this risk when selecting an initial dose and when making dose adjustments [see Warnings and Precautions (5.2)].
- NUCYNTA ER is administered orally twice daily (approximately every 12 hours).
- Instruct patients to swallow NUCYNTA ER tablets whole, one tablet at a time, with enough water to ensure complete swallowing immediately after placing in the mouth.
- Crushing, chewing, or dissolving NUCYNTA ER tablets will result in uncontrolled delivery of tapentadol and can lead to overdose or death [see Warnings and Precautions (5.1)].
- Discontinue all other tapentadol and tramadol products when beginning and while taking NUCYNTA ER [see Warnings and Precautions (5.7)].
- Although the maximum approved total daily dose of NUCYNTA immediate-release formulation is 600 mg per day, the maximum total daily dose of NUCYNTA ER is 500 mg.
- Do not exceed a total daily dose of NUCYNTA ER of 500 mg.

2.2 Patient Access to an Opioid Overdose Reversal Agent for the Emergency Treatment of Opioid Overdose

Inform patients and caregivers about opioid overdose reversal agents (e.g., naloxone, nalmefene). Discuss the importance of having access to an opioid overdose reversal agent, especially if the patient has risk factors for overdose (e.g., concomitant use of CNS depressants, a history of opioid use disorder, or prior opioid overdose) or if there are household members (including children) or other close contacts at risk for accidental ingestion or opioid overdose. The presence of risk factors for overdose should not prevent the management of pain in any patient [see Warnings and Precautions (5.1, 5.2, 5.3)].

Discuss the options for obtaining an opioid overdose reversal agent (e.g., prescription, over-the-counter, or as part of a community-based program) [see Warnings and Precautions (5.2)].

There are important differences among the opioid overdose reversal agents, such as route of administration, product strength, approved patient age range, and pharmacokinetics. Be familiar with these differences, as outlined in the approved labeling for those products, prior to recommending or prescribing such an agent.

2.3 Initial Dosage

It is safer to underestimate a patient's 24-hour oral tapentadol dosage and provide rescue medication (e.g., immediate-release opioid) than to overestimate the 24-hour oral tapentadol requirements which could result in an adverse reaction due to an overdose. While useful tables of opioid equivalents are readily available, there is inter-patient variability in the potency of opioid drugs and opioid formulations. Frequently reevaluate patients for signs and symptoms of opioid withdrawal and for signs of oversedation/toxicity after converting patients to NUCYNTA ER.

Use of NUCYNTA ER in Patients who are not Opioid Tolerant

The starting dose for patients who are not opioid tolerant is NUCYNTA ER 50 mg orally twice daily (approximately every 12 hours). Use of higher starting doses in patients who are not opioid tolerant may cause fatal respiratory depression.

Conversion from Tapentadol Immediate-Release (IR) products to NUCYNTA ER

Patients can be converted from tapentadol IR to NUCYNTA ER using the equivalent total daily dose of tapentadol IR and dividing it into two equal doses of NUCYNTA ER separated by approximately 12-hour intervals. As an example, a patient receiving 50 mg of tapentadol IR four times per day (200 mg/day) may be converted to 100 mg NUCYNTA ER twice a day.

Conversion from Methadone to NUCYNTA ER

Frequent evaluation is of particular importance when converting from methadone to other opioid agonists. The ratio between methadone and other opioid agonists may vary widely as a function of previous dose exposure. Methadone has a long half-life and can accumulate in the plasma.

Conversion from Other Opioid Analgesics to NUCYNTA ER

When NUCYNTA ER therapy is initiated, discontinue all other opioid analgesics other than those used on an as needed basis for breakthrough pain when appropriate. There are no established conversion ratios for conversion from other opioids to NUCYNTA ER defined by clinical trials. Initiate dosing using NUCYNTA ER 50 mg orally every 12 hours.

2.4 Titration and Maintenance of Therapy

Individually titrate NUCYNTA ER to a dose that provides adequate analgesia and minimizes adverse reactions. Continually reevaluate patients receiving NUCYNTA ER to assess the maintenance of pain control, signs and symptoms of opioid withdrawal, and other adverse reactions, as well as to reassess for the development of addiction, abuse, or misuse [see Warnings and Precautions (5.1, 5.14)]. Frequent communication is important among the prescriber, other members of the healthcare team, the patient, and the caregiver/family during periods of changing analgesic requirements, including initial titration. During use of opioid therapy for an extended period of time, periodically reassess the continued need for opioid analgesics.

Patients who experience breakthrough pain may require a dosage adjustment of NUCYNTA ER or may need rescue medication with an appropriate dose of an immediate-release analgesic.

If the level of pain increases after dose stabilization, attempt to identify the source of increased pain before increasing the NUCYNTA ER dosage. If after increasing the dosage, unacceptable opioid-related adverse reactions are observed (including an increase in pain after a dosage increase), consider reducing the dosage [see Warnings and Precautions (5)]. Adjust the dosage to obtain an appropriate balance between management of pain and opioid-related adverse reactions.

Titrate patients to adequate analgesia with dose increases of 50 mg no more than twice daily every three days. In clinical studies, efficacy with NUCYNTA ER was demonstrated relative to placebo in the dosage range of 100 mg to 250 mg twice daily [see Clinical Studies(14)].

2.5 Dosage Modification in Patients with Hepatic Impairment

The use of NUCYNTA ER in patients with severe hepatic impairment (Child-Pugh Score 10-15) is not recommended [see Warnings and Precautions (5.16)].

In patients with moderate hepatic impairment (Child-Pugh Score 7 to 9), initiate treatment using 50 mg NUCYNTA ER, administer no more frequently than once every 24 hours, and regularly evaluate for respiratory and central nervous system depression, particularly during initiation and titration of NUCYNTA ER. The maximum recommended dose for patients with moderate hepatic impairment is 100 mg of NUCYNTA ER per day. Regularly evaluate patients for respiratory and central nervous system depression [see Clinical Pharmacology (12.2)].

No dosage adjustment is recommended in patients with mild hepatic impairment (Child-Pugh Score 5 to 6) [see Warnings and Precautions (5.16), Use in Specific Populations (8.6), Clinical Pharmacology (12.3)].

2.6 Safe Reduction or Discontinuation of NUCYNTA ER

Do not rapidly reduce or abruptly discontinue NUCYNTA ER in patients who may be physically dependent on opioids. Rapid reduction or abrupt discontinuation of opioid analgesics in patients who are physically dependent on opioids has resulted in serious withdrawal symptoms, uncontrolled pain, and suicide. Rapid reduction or abrupt discontinuation has also been associated with attempts to find other sources of opioid analgesics, which may be confused with drug-seeking for abuse.

Patients may also attempt to treat their pain or withdrawal symptoms with illicit opioids, such as heroin, and other substances.

When a decision has been made to decrease the dose or discontinue therapy in an opioid-dependent patient taking NUCYNTA ER, there are a variety of factors that should be considered, including the total daily dose of opioid (including NUCYNTA ER) the patient has been taking, the duration of treatment, the type of pain being treated, and the physical and psychological attributes of the patient. It is important to ensure ongoing care of the patient and to agree on an appropriate tapering schedule and follow-up plan so that patient and provider goals and expectations are clear and realistic. When opioid analgesics are being discontinued due to a suspected substance use disorder, evaluate and treat the patient, or refer for evaluation and treatment of the substance use disorder. Treatment should include evidence-based approaches, such as medication assisted treatment of opioid use disorder. Complex patients with co-morbid pain and substance use disorders may benefit from referral to a specialist.

There are no standard opioid tapering schedules that are suitable for all patients. Good clinical practice dictates a patient-specific plan to taper the dose of the opioid gradually. For patients on NUCYNTA ER who are physically opioid-dependent, initiate the taper by a small enough increment (e.g., no greater than 10% to 25% of the total daily dose) to avoid withdrawal symptoms, and proceed with dose-lowering at an interval of every 2 to 4 weeks. Patients who have been taking opioids for briefer periods of time may tolerate a more rapid taper.

It may be necessary to provide the patient with lower dosage strengths to accomplish a successful taper. Reassess the patient frequently to manage pain and withdrawal symptoms, should they emerge. Common withdrawal symptoms include restlessness, lacrimation, rhinorrhea, yawning, perspiration, chills, myalgia, and mydriasis. Other signs and symptoms also may develop, including irritability, anxiety, backache, joint pain, weakness, abdominal cramps, insomnia, nausea, anorexia, vomiting, diarrhea, or increased blood pressure, respiratory rate, or heart rate. If withdrawal symptoms arise, it may be necessary to pause the taper for a period of time or raise the dose of the opioid analgesic to the previous dose, and then proceed with a slower taper. In addition, evaluate patients for any changes in mood, emergence of suicidal thoughts, or use of other substances.

When managing patients taking opioid analgesics, particularly those who have been treated for an extended period of time and/or with high doses for chronic pain, ensure that a multimodal approach to pain management, including mental health support (if needed), is in place prior to initiating an opioid analgesic taper. A multimodal approach to pain management may optimize the treatment of chronic pain, as well as assist with the successful tapering of the opioid analgesic [see Warnings and Precautions (5.14), Drug Abuse and Dependence (9.3)].

3 DOSAGE FORMS AND STRENGTHS

NUCYNTA ER 50 mg, 100 mg, 150 mg, 200 mg and 250 mg extended-release tablets are available in the following colors and prints:

- 50 mg extended-release tablets are white oblong-shaped with a black print "OMJ 50" on one side
- 100 mg extended-release tablets are light-blue oblong-shaped with a black print "OMJ 100" on one side
- 150 mg extended-release tablets are blue-green oblong-shaped with a black print "OMJ 150" on one side
- 200 mg extended-release tablets are blue oblong-shaped with a depression in the middle running lengthwise on each side and a black print "OMJ 200" on one side
- 250 mg extended-release tablets are dark blue oblong-shaped with a depression in the middle running lengthwise on each side and a white print "OMJ 250" on one side.

4 CONTRAINDICATIONS

NUCYNTA ER is contraindicated in patients with:

- Significant respiratory depression
- Acute or severe bronchial asthma or hypercarbia in an unmonitored setting or in the absence of resuscitative equipment
- Known or suspected gastrointestinal obstruction, including paralytic ileus
- Hypersensitivity (e.g., anaphylaxis, angioedema) to tapentadol or to any other ingredients of the product [see Adverse Reactions (6.2)].
- Concurrent use of monoamine oxidase inhibitors (MAOIs) or use of MAOIs within the last 14 days [see Drug Interactions (7)].

5 WARNINGS AND PRECAUTIONS

5.1 Addiction, Abuse, and Misuse

NUCYNTA ER contains tapentadol, a Schedule II controlled substance. As an opioid, NUCYNTA ER exposes users to the risks of addiction, abuse, and misuse.

Although the risk of addiction in any individual is unknown, it can occur in patients appropriately prescribed NUCYNTA ER. Addiction can occur at recommended doses and if the drug is misused or abused. The risk of opioid-related overdose or overdose-related death is increased with higher opioid doses, and this risk persists over the course of therapy. In postmarketing studies, addiction, abuse, misuse, and fatal and non-fatal opioid overdose were observed in patients with long-term opioid use [see Adverse Reactions (6.2)].

Assess each patient's risk for opioid addiction, abuse, or misuse prior to prescribing NUCYNTA ER, and reassess all patients receiving NUCYNTA ER for the development of these behaviors and conditions. Risks are increased in patients with a personal or family history of substance abuse (including drug or alcohol abuse or addiction) or mental illness (e.g., major depression). The potential for these risks should not, however, prevent the prescribing of NUCYNTA ER for the proper management of pain in any given patient. Patients at increased risk may be prescribed opioids such as NUCYNTA ER but use in such patients necessitates intensive counseling about the risks and proper use of NUCYNTA ER along with frequent reevaluation for signs of addiction, abuse, and misuse. Consider recommending or prescribing an opioid overdose reversal agent [see Dosage and Administration (2.2), Warnings and Precautions (5.2)].

Abuse or misuse of NUCYNTA ER by crushing, chewing, snorting, or injecting the dissolved product will result in the uncontrolled delivery of tapentadol and can result in overdose and death [see Overdosage (10)].

Opioids are sought for nonmedical use and are subject to diversion from legitimate prescribed use. Consider these risks when prescribing or dispensing NUCYNTA ER. Strategies to reduce these risks include prescribing the drug in the smallest appropriate quantity and advising the patient on careful storage of the drug during the course of treatment and the proper disposal of unused drug. Contact the local state professional licensing board or state-controlled substances authority for information on how to prevent and detect abuse or diversion of this product.

5.2 Life-Threatening Respiratory Depression

Serious, life-threatening, or fatal respiratory depression has been reported with the use of opioids, even when used as recommended. Respiratory depression, if not immediately recognized and treated, may lead to respiratory arrest and death. Management of respiratory depression may include close observation, supportive measures, and use of opioid overdose reversal agents, depending on the patient's clinical status [see Overdosage (10)].

Carbon dioxide (CO2) retention from opioid-induced respiratory depression can exacerbate the sedating effects of opioids.

While serious, life-threatening, or fatal respiratory depression can occur at any time during the use of NUCYNTA ER, the risk is greatest during the initiation of therapy or following a dosage increase.

To reduce the risk of respiratory depression, proper dosing and titration of NUCYNTA ER are essential [see Dosage and Administration (2)]. Overestimating the NUCYNTA ER dosage when converting patients from another opioid product can result in fatal overdose with the first dose.

Accidental ingestion of even one dose of NUCYNTA ER, especially by children, can result in respiratory depression and death due to an overdose of tapentadol.

Educate patients and caregivers on how to recognize respiratory depression and emphasize the importance of calling 911 or getting emergency medical help right away in the event of a known or suspected overdose.

Opioids can cause sleep-related breathing disorders including central sleep apnea (CSA) and sleep-related hypoxemia. Opioid use increases the risk of CSA in a dose-dependent fashion. In patients who present with CSA, consider decreasing the opioid dosage using best practices for opioid taper [see Dosage and Administration (2.6)].

Patient Access to an Opioid Overdose Reversal Agent for the Emergency Treatment of Opioid Overdose

Inform patients and caregivers about opioid overdose reversal agents (e.g., naloxone, nalmefene). Discuss the importance of having access to an opioid overdose reversal agent, especially if the patient has risk factors for overdose (e.g., concomitant use of CNS depressants, a history of opioid use disorder, or prior opioid overdose) or if there are household members (including children) or other close contacts at risk for accidental ingestion or opioid overdose. The presence of risk factors for overdose should not prevent the management of pain in any patient [see Warnings and Precautions (5.1, 5.3)].

Discuss the options for obtaining an opioid overdose reversal agent (e.g., prescription, over-the-counter, or as part of a community-based program).

There are important differences among the opioid overdose reversal agents, such as route of administration, product strength, approved patient age range, and pharmacokinetics. Be familiar with these differences, as outlined in the approved labeling for those products, prior to recommending or prescribing such an agent.

Educate patients and caregivers on how to recognize respiratory depression, and how to use an opioid overdose reversal agent for the emergency treatment of opioid overdose. Emphasize the importance of calling 911 or getting emergency medical help, even if an opioid overdose reversal agent is administered [see Dosage and Administration (2.2), Warnings and Precautions (5.1, 5.3), Overdosage (10)].

5.3 Risks from Concomitant Use with Benzodiazepines or Other CNS Depressants

Patients must not consume alcoholic beverages or prescription or non-prescription products containing alcohol while on NUCYNTA ER therapy. The co-ingestion of alcohol with NUCYNTA ER may result in increased plasma tapentadol levels and a potentially fatal overdose of tapentadol [see Clinical Pharmacology (12.3)].

Profound sedation, respiratory depression, coma, and death may result from the concomitant use of NUCYNTA ER with benzodiazepines and/or other CNS depressants, including alcohol (e.g., non-benzodiazepine sedatives/hypnotics, anxiolytics, tranquilizers, muscle relaxants, general anesthetics, antipsychotics, gabapentinoids [gabapentin or pregabalin], , and other opioids). Because of these risks, reserve concomitant prescribing of these drugs for use in patients for whom alternative treatment options are inadequate.

Observational studies have demonstrated that concomitant use of opioid analgesics and benzodiazepines increases the risk of drug-related mortality compared to use of opioid analgesics alone. Because of similar pharmacological properties, it is reasonable to expect similar risk with the concomitant use of other CNS depressant drugs with opioid analgesics [see Drug Interactions (7)].

If the decision is made to prescribe a benzodiazepine or other CNS depressant concomitantly with an opioid analgesic, prescribe the lowest effective dosages and minimum durations of concomitant use. In patients already receiving an opioid analgesic, prescribe a lower initial dose of the benzodiazepine or other CNS depressant than indicated in the absence of an opioid, and titrate based on clinical response. If an opioid analgesic is initiated in a patient already taking a benzodiazepine or other CNS depressant, prescribe a lower initial dose of the opioid analgesic, and titrate based on clinical response. Inform patients and caregivers of this potential interaction and educate them on the signs and symptoms of respiratory depression (including sedation).

If concomitant use is warranted, consider recommending or prescribing an opioid overdose reversal agent [see Dosage and Administration (2.2), Warnings and Precautions (5.2), Overdosage (10)].

Advise both patients and caregivers about the risks of respiratory depression and sedation when NUCYNTA ER is used with benzodiazepines or other CNS depressants (including alcohol and illicit drugs). Advise patients not to drive or operate heavy machinery until the effects of concomitant use of the benzodiazepine or other CNS depressants have been determined. Screen patients for risk of substance use disorders, including opioid abuse and misuse, and warn them of the risk for overdose and death associated with the use of additional CNS depressants including alcohol and illicit drugs [see Drug Interactions (7)].

5.4 Neonatal Opioid Withdrawal Syndrome

Use of NUCYNTA ER for an extended period of time during pregnancy can result in withdrawal in the neonate. Neonatal opioid withdrawal syndrome, unlike opioid withdrawal syndrome in adults, may be life-threatening if not recognized and treated, and requires management according to protocols developed by neonatology experts.

Observe newborns for signs of neonatal opioid withdrawal syndrome and manage accordingly. Advise pregnant women using opioids for an extended period of time of the risk of neonatal opioid withdrawal syndrome and ensure that appropriate treatment will be available [see Use in Specific Populations (8.1)].

5.5 Opioid Analgesic Risk Evaluation and Mitigation Strategy (REMS)

To ensure that the benefits of opioid analgesics outweigh the risks of addiction, abuse, and misuse, the Food and Drug Administration (FDA) has required a Risk Evaluation and Mitigation Strategy (REMS) for these products. Under the requirements of the REMS, drug companies with approved opioid analgesic products must make REMS-compliant education programs available to healthcare providers. Healthcare providers are strongly encouraged to do all of the following:

- Complete a REMS-compliant education program offered by an accredited provider of continuing education (CE) or another education program that includes all the elements of the FDA Education Blueprint for Health Care Providers Involved in the Management or Support of Patients with Pain.
- Discuss the safe use, serious risks, and proper storage and disposal of opioid analgesics with patients and/or their caregivers every time these medicines are prescribed. The Patient Counseling Guide (PCG) can be obtained at this link: www.fda.gov/OpioidAnalgesicREMSPCG.
- Emphasize to patients and their caregivers the importance of reading the Medication Guide that they will receive from their pharmacist every time an opioid analgesic is dispensed to them.
- Consider using other tools to improve patient, household, and community safety, such as patient- prescriber agreements that reinforce patient-prescriber responsibilities.

To obtain further information on the opioid analgesic REMS and for a list of accredited REMS CME/CE, call 1-800-503-0784, or log on to www.opioidanalgesicrems.com. The FDA Blueprint can be found at www.fda.gov/OpioidAnalgesicREMSBlueprint.

5.6 Opioid-Induced Hyperalgesia and Allodynia

Opioid-Induced Hyperalgesia (OIH) occurs when an opioid analgesic paradoxically causes an increase in pain, or an increase in sensitivity to pain. This condition differs from tolerance, which is the need for increasing doses of opioids to maintain a defined effect [see Dependence (9.3)]. Symptoms of OIH include (but may not be limited to) increased levels of pain upon opioid dosage increase, decreased levels of pain upon opioid dosage decrease, or pain from ordinarily non-painful stimuli (allodynia). These symptoms may suggest OIH only if there is no evidence of underlying disease progression, opioid tolerance, opioid withdrawal, or addictive behavior.

Cases of OIH have been reported, both with short-term and longer-term use of opioid analgesics. Though the mechanism of OIH is not fully understood, multiple biochemical pathways have been implicated. Medical literature suggests a strong biologic plausibility between opioid analgesics and OIH and allodynia. If a patient is suspected to be experiencing OIH, carefully consider appropriately decreasing the dose of the current opioid analgesic or opioid rotation (safely switching the patient to a different opioid moiety) [see Dosage and Administration (2.6), Warnings and Precautions (5.14)].

5.7 Serotonin Syndrome with Concomitant Use of Serotonergic Drugs

Cases of serotonin syndrome, a potentially life-threatening condition, have been reported during concomitant use of tapentadol with serotonergic drugs. Serotonergic drugs include selective serotonin reuptake inhibitors (SSRIs), serotonin and norepinephrine reuptake inhibitors (SNRIs), tricyclic antidepressants (TCAs), triptans, 5-HT3 receptor antagonists, drugs that affect the serotonergic neurotransmitter system (e.g., mirtazapine, trazodone, tramadol), certain muscle relaxants (i.e., cyclobenzaprine, metaxalone), and drugs that impair metabolism of serotonin (including monoamine oxidase inhibitors, both those intended to treat psychiatric disorders and also others, such as linezolid and intravenous methylene blue) [see Drug Interactions (7)]. This may occur within the recommended dosage range.

Serotonin syndrome symptoms may include mental status changes (e.g., agitation, hallucinations, coma), autonomic instability (e.g., tachycardia, labile blood pressure, hyperthermia), neuromuscular aberrations (e.g., hyperreflexia, incoordination, rigidity), and/or gastrointestinal symptoms (e.g., nausea, vomiting, diarrhea). The onset of symptoms generally occurs within several hours to a few days of concomitant use but may occur later than that. Discontinue NUCYNTA ER if serotonin syndrome is suspected.

5.8 Life-Threatening Respiratory Depression in Patients with Chronic Pulmonary Disease or in Elderly, Cachectic, or Debilitated Patients

The use of NUCYNTA ER in patients with acute or severe bronchial asthma in an unmonitored setting or in the absence of resuscitative equipment is contraindicated.

Patients with Chronic Pulmonary Disease: NUCYNTA ER treated patients with significant chronic obstructive pulmonary disease or cor pulmonale, and those with a substantially decreased respiratory reserve, hypoxia, hypercapnia, or pre-existing respiratory depression are at increased risk of decreased respiratory drive including apnea, even at recommended dosages of NUCYNTA ER [see Warnings and Precautions (5.2)].

Elderly, Cachectic, or Debilitated Patients: Life-threatening respiratory depression is more likely to occur in elderly, cachectic, or debilitated patients because they may have altered pharmacokinetics or altered clearance compared to younger, healthier patients [see Warnings and Precautions (5.2)].

Regularly evaluate patients, particularly when initiating and titrating NUCYNTA ER and when NUCYNTA ER is given concomitantly with other drugs that depress respiration [see Warnings and Precautions (5.2), Drug Interactions (7)]. Alternatively, consider the use of non-opioid analgesics in these patients.

5.9 Adrenal Insufficiency

Cases of adrenal insufficiency have been reported with opioid use, more often following greater than one month of use. Presentation of adrenal insufficiency may include non-specific symptoms and signs including nausea, vomiting, anorexia, fatigue, weakness, dizziness, and low blood pressure. If adrenal insufficiency is suspected, confirm the diagnosis with diagnostic testing as soon as possible. If adrenal insufficiency is diagnosed, treat with physiologic replacement doses of corticosteroids. Wean the patient off of the opioid to allow adrenal function to recover and continue corticosteroid treatment until adrenal function recovers. Other opioids may be tried as some cases reported use of a different opioid without recurrence of adrenal insufficiency. The information available does not identify any particular opioids as being more likely to be associated with adrenal insufficiency.

5.10 Severe Hypotension

NUCYNTA ER may cause severe hypotension including orthostatic hypotension and syncope in ambulatory patients. There is an increased risk in patients whose ability to maintain blood pressure has already been compromised by a reduced blood volume or concurrent administration of certain CNS depressant drugs (e.g., phenothiazines or general anesthetics) [see Drug Interactions (7)]. Regularly evaluate these patients for signs of hypotension after initiating or titrating the dosage of NUCYNTA ER. In patients with circulatory shock, NUCYNTA ER may cause vasodilation that can further reduce cardiac output and blood pressure. Avoid the use of NUCYNTA ER in patients with circulatory shock.

5.11 Risks of Use in Patients with Increased Intracranial Pressure, Brain Tumors, Head Injury, or Impaired Consciousness

In patients who may be susceptible to the intracranial effects of CO2 retention (e.g., those with evidence of increased intracranial pressure or brain tumors), NUCYNTA ER may reduce respiratory drive, and the resultant CO2 retention can further increase intracranial pressure.

Monitor such patients for signs of sedation and respiratory depression, particularly when initiating therapy with NUCYNTA ER.

Opioids may also obscure the clinical course in a patient with a head injury. Avoid the use of NUCYNTA ER in patients with impaired consciousness or coma.

5.12 Risks of Gastrointestinal Complications

NUCYNTA ER is contraindicated in patients with known or suspected gastrointestinal obstruction, including paralytic ileus.

The tapentadol in NUCYNTA ER may cause spasm of the sphincter of Oddi. Opioids may cause increases in serum amylase. Regularly evaluate patients with biliary tract disease, including acute pancreatitis, for worsening symptoms.

Cases of opioid-induced esophageal dysfunction (OIED) have been reported in patients taking opioids. The risk of OIED may increase as the dose and/or duration of opioids increases. Regularly evaluate patients for signs and symptoms of OIED (e.g., dysphagia, regurgitation, non-cardiac chest pain) and, if necessary, adjust opioid therapy as clinically appropriate [see Clinical Pharmacology (12.2)].

5.13 Increased Risk of Seizures in Patients with Seizure Disorders

The tapentadol in NUCYNTA ER may increase the frequency of seizures in patients with seizure disorders and may increase the risk of seizures occurring in other clinical settings associated with seizures. Regularly evaluate patients with a history of seizure disorders for worsened seizure control during NUCYNTA ER therapy.

5.14 Withdrawal

Do not rapidly reduce or abruptly discontinue NUCYNTA ER in a patient physically dependent on opioids. When discontinuing NUCYNTA ER in a physically dependent patient, gradually taper the dosage. Rapid tapering of tapentadol in a patient physically dependent on opioids may lead to a withdrawal syndrome and return of pain [see Dosage and Administration (2.6), Drug Abuse and Dependence (9.3)].

Additionally, avoid the use of mixed agonist/antagonist (e.g., pentazocine, nalbuphine, and butorphanol) or partial agonist (e.g., buprenorphine) analgesics in patients who have received or are receiving a course of therapy with a full opioid agonist analgesic, including NUCYNTA ER. In these patients, mixed agonists/antagonists and partial agonist analgesics may reduce the analgesic effect and/or may precipitate withdrawal symptoms [see Drug Interactions (7)].

5.15 Risks of Driving and Operating Machinery

NUCYNTA ER may impair the mental or physical abilities needed to perform potentially hazardous activities such as driving a car or operating machinery. Warn patients not to drive or operate dangerous machinery unless they are tolerant to the effects of NUCYNTA ER and know how they will react to the medication.

5.16 Risk of Toxicity in Patients with Hepatic Impairment

A study with an immediate-release formulation of tapentadol in subjects with hepatic impairment showed higher serum concentrations of tapentadol than in those with normal hepatic function. Avoid use of NUCYNTA ER in patients with severe hepatic impairment. Reduce the dose of NUCYNTA ER in patients with moderate hepatic impairment [see Dosage and Administration (2.5) and Clinical Pharmacology (12.3)].

Frequently evaluate patients with moderate hepatic impairment for respiratory and central nervous system depression when initiating and titrating NUCYNTA ER.

5.17 Risk of Toxicity in Patients with Renal Impairment

Use of NUCYNTA ER in patients with severe renal impairment is not recommended due to accumulation of a metabolite formed by glucuronidation of tapentadol. The clinical relevance of the elevated metabolite is not known [see Clinical Pharmacology (12.3)].

6 ADVERSE REACTIONS

The following serious adverse reactions are described, or described in greater detail, in other sections:

- Addiction, Abuse, and Misuse [see Warnings and Precautions (5.1)]
- Life-Threatening Respiratory Depression [see Warnings and Precautions (5.2)]
- Interaction with Benzodiazepine or Other CNS Depressants [see Warnings and Precautions (5.3)]
- Neonatal Opioid Withdrawal Syndrome [see Warnings and Precautions (5.4)]
- Opioid-Induced Hyperalgesia and Allodynia [see Warnings and Precautions (5.6)]
- Serotonin Syndrome [see Warnings and Precautions (5.7)]
- Adrenal Insufficiency [see Warnings and Precautions (5.9)]
- Severe Hypotension [see Warnings and Precautions (5.10)]
- Gastrointestinal Adverse Reactions [see Warnings and Precautions (5.12)]
- Seizures [see Warnings and Precautions (5.13)]
- Withdrawal [see Warnings and Precautions (5.14)]

6.1 Clinical Trial Experience

Because clinical trials are conducted under widely varying conditions, adverse reaction rates observed in the clinical trials of a drug cannot be directly compared to rates in the clinical trials of another drug and may not reflect the rates observed in clinical practice.

Commonly-Observed Adverse Reactions in Clinical Studies with NUCYNTA ER in Patients with Chronic Pain due to Low Back Pain or Osteoarthritis

The safety data described in Table 1 below are based on three pooled, randomized, double-blind, placebo-controlled, parallel group, 15-week studies of NUCYNTA ER (dosed 100 to 250 mg BID after a 50 mg BID starting dose) in patients with chronic pain due to low back pain (LBP) and osteoarthritis (OA). These trials included 980 NUCYNTA ER-treated patients and 993 placebo-treated patients. The mean age was 57 years old; 63% were female and 37% were male; 83% were White, 10% were Black, and 5% were Hispanic. The most common adverse reactions (reported by ≥10% in any NUCYNTA ER dose group) were: nausea, constipation, dizziness, headache, and somnolence.

The most common reasons for discontinuation due to adverse reactions in eight Phase 2/3 pooled studies reported by ≥1% in any NUCYNTA ER dose group for NUCYNTA ER- and placebo-treated patients were nausea (4% vs. 1%), dizziness (3% vs. <1%), vomiting (3% vs. <1%), somnolence (2% vs. <1%), constipation (1% vs. <1%), headache (1% vs. <1%), and fatigue (1% vs. <1%), respectively.

Table 1. Adverse Drug Reactions Reported by ≥ 1% of NUCYNTA ER-Treated Patients and Greater than Placebo- Treated Patients in Pooled Parallel-Group Trials [MedDRA preferred terms. The trials included forced titration during the first week of dosing.]
 | NUCYNTA ER 50 to 250 mg BID [NUCYNTA ER dosed between 100 and 250 mg BID after a starting dose of 50 mg BID] (n=980) | Placebo (n=993)
Nausea | 21% | 7%
Constipation | 17% | 7%
Dizziness | 17% | 6%
Headache | 15% | 13%
Somnolence | 12% | 4%
Fatigue | 9% | 4%
Vomiting | 8% | 3%
Dry mouth | 7% | 2%
Hyperhidrosis | 5% | <1%
Pruritus | 5% | 2%
Insomnia | 4% | 2%
Dyspepsia | 3% | 2%
Lethargy | 2% | <1%
Asthenia | 2% | <1%
Anxiety | 2% | 1%
Decreased appetite | 2% | <1%
Vertigo | 2% | <1%
Hot flush | 2% | <1%
Disturbance in attention | 1% | <1%
Tremor | 1% | <1%
Chills | 1% | 0%
Abnormal dreams | 1% | <1%
Depression | 1% | <1%
Vision blurred | 1% | <1%
Erectile dysfunction | 1% | <1%

Commonly-Observed Adverse Reactions in Clinical Studies with NUCYNTA ER in Patients with Neuropathic Pain Associated with Diabetic Peripheral Neuropathy

The types of adverse reactions seen in the studies of patients with painful diabetic peripheral neuropathy (DPN) were similar to what was seen in the low back pain and osteoarthritis trials. The safety data described in Table 2 below are based on two pooled, randomized withdrawal, double-blind, placebo-controlled, 12-week studies of NUCYNTA ER (dosed 100 to 250 mg BID) in patients with neuropathic pain associated with diabetic peripheral neuropathy. These trials included 1040 NUCYNTA ER-treated patients and 343 placebo- treated patients. The mean age was 60 years old; 40% were female and 60% were male; 76% were White, 12% were Black, and 12% were "Other". The most commonly reported ADRs (incidence ≥10% in NUCYNTA ER-treated subjects) were: nausea, constipation, vomiting, dizziness, somnolence, and headache.

Table 2 lists the common adverse reactions reported in 1% or more of NUCYNTA ER-treated patients and greater than placebo-treated patients with neuropathic pain associated with diabetic peripheral neuropathy in the two pooled studies.

Table 2. Adverse Drug Reactions Reported by ≥ 1% of NUCYNTA ER-Treated Patients and Greater than Placebo-Treated Patients in Pooled Trials (Studies DPN-1 and DPN-2) [MedDRA preferred terms.]
 | NUCYNTA ER 50 to 250 mg BID [NUCYNTA ER dosed between 100 and 250 mg BID after a starting dose of 50 mg BID. It includes ADR reported in the open-label titration period for all subjects and in the double-blind maintenance period for the subjects who were randomized to NUCYNTA ER.] (n=1040) | Placebo [It includes ADR reported in the double-blind maintenance period for the subjects who were randomized to placebo after receiving NUCYNTA ER during the open-label titration period.] (n=343)
Nausea | 27% | 8%
Dizziness | 18% | 2%
Somnolence | 14% | <1%
Constipation | 13% | <1%
Vomiting | 12% | 3%
Headache | 10% | 5%
Fatigue | 9% | <1%
Pruritus | 8% | 0%
Dry mouth | 7% | <1%
Diarrhea | 7% | 5%
Decreased appetite | 6% | <1%
Anxiety | 5% | 4%
Insomnia | 4% | 3%
Hyperhidrosis | 3% | 2%
Hot flush | 3% | 2%
Tremor [Tremor was observed in 3.4% of NUCYNTA ER-treated subjects vs. 3.2% in placebo group, chills- in 1.3% vs.1.2% in placebo, and feeling cold- in 1.3% vs.1.2% in placebo.] | 3% | 3%
Abnormal dreams | 2% | 0%
Lethargy | 2% | 0%
Asthenia | 2% | <1%
Irritability | 2% | 1%
Dyspnea | 1% | 0%
Nervousness | 1% | 0%
Sedation | 1% | 0%
Vision blurred | 1% | 0%
Pruritus generalized | 1% | 0%
Vertigo | 1% | <1%
Abdominal discomfort | 1% | <1%
Hypotension | 1% | <1%
Dyspepsia | 1% | <1%
Hypoesthesia | 1% | <1%
Depression | 1% | <1%
Rash | 1% | <1%
Chills | 1% | 1%
Feeling cold | 1% | 1%
Drug withdrawal syndrome | 1% | <1%

Other Adverse Reactions Observed During the Premarketing Evaluation of NUCYNTA ER

The following additional adverse drug reactions occurred in less than 1% of NUCYNTA ER-treated patients in ten Phase 2/3 clinical studies:

Nervous system disorders: paresthesia, balance disorder, syncope, memory impairment, mental impairment, depressed level of consciousness, dysarthria, presyncope, coordination abnormal

Gastrointestinal disorders: impaired gastric emptying

General disorders and administration site conditions: feeling abnormal, feeling drunk

Psychiatric disorders: perception disturbances, disorientation, confusional state, agitation, euphoric mood, drug dependence, thinking abnormal, nightmare

Skin and subcutaneous tissue disorders: urticaria

Metabolism and nutrition disorders: weight decreased

Cardiac disorders: heart rate increased, palpitations, heart rate decreased, left bundle branch block

Vascular disorder: blood pressure decreased

Respiratory, thoracic and mediastinal disorders: respiratory depression

Renal and urinary disorders: urinary hesitation, pollakiuria

Reproductive system and breast disorders: sexual dysfunction

Eye disorders: visual disturbance

Immune system disorders: drug hypersensitivity

6.2 Postmarketing Experience

The following adverse reactions have been identified during post approval use of tapentadol. Because these reactions are reported voluntarily from a population of uncertain size, it is not always possible to reliably estimate their frequency or establish a causal relationship to drug exposure.

Psychiatric disorders: hallucination, suicidal ideation, panic attack

Serotonin syndrome: Cases of serotonin syndrome, a potentially life-threatening condition, have been reported during concomitant use of opioids with serotonergic drugs.

Adrenal insufficiency: Cases of adrenal insufficiency have been reported with opioid use, more often following greater than one month of use.

Anaphylaxis: Anaphylaxis has been reported with ingredients contained in NUCYNTA ER.

Androgen deficiency: Cases of androgen deficiency have occurred with use of opioids for an extended period of time [see Clinical Pharmacology (12.2)].

Hyperalgesia and Allodynia: Cases of hyperalgesia and allodynia have been reported with opioid therapy of any duration [see Warnings and Precautions (5.6)]

Hypoglycemia: Cases of hypoglycemia have been reported in patients taking opioids. Most reports were in patients with at least one predisposing risk factor (e.g., diabetes).

Opioid-induced esophageal dysfunction (OIED): Cases of OIED have been reported in patients taking opioids, and may occur more frequently in patients taking higher doses of opioid, and/or in patients taking opioids longer term [see Warnings and Precautions (5.12)].

Adverse Reactions from Observational Studies

A prospective, observational cohort study estimated the risks of addiction, abuse, and misuse in patients initiating long-term use of Schedule II opioid analgesics between 2017 and 2021. Study participants included in one or more analyses had been enrolled in selected insurance plans or health systems for at least one year, were free of at least one outcome at baseline, completed a minimum number of follow-up assessments, and either: 1) filled multiple extended-release/long-acting opioid analgesic prescriptions during a 90-day period (n=978); or 2) filled any Schedule II opioid analgesic prescriptions covering at least 70 of 90 days (n=1,244). Those included also had no dispensing of the qualifying opioids in the previous 6 months.

Over 12 months:

- approximately 1% to 6% of participants across the two cohorts newly met criteria for addiction, as assessed with two validated interview-based measures of moderate-to-severe opioid use disorder based on Diagnostic and Statistical Manual of Mental Disorders, Fifth Edition (DSM-5) criteria, and
- approximately 9% and 22% of participants across the two cohorts newly met criteria for prescription opioid abuse and misuse [defined in Drug Abuse and Dependence (9.2)], respectively, as measured with a validated self-reported instrument.

A retrospective, observational cohort study estimated the risk of opioid involved overdose or opioid overdose-related death in patients with new long-term use of Schedule II opioid analgesics from 2006 through 2016 (n=220,249). Included patients had been enrolled in either one of two commercial insurance programs, one managed care program, or one Medicaid program for at least 9 months. New long-term use was defined as having Schedule II opioid analgesic prescriptions covering at least 70 days' supply over the 3 months prior to study entry and none during the preceding 6 months. Patients were excluded if they had an opioid-involved overdose in the 9 months prior to study entry. Overdose was measured using a validated medical code-based algorithm with linkage to the National Death Index database. The 5-year cumulative incidence estimates for opioid-involved overdose or opioid overdose-related death ranged from approximately 1.5% to 4% across study sites, counting only the first event during follow-up. Approximately 17% of first opioid overdoses observed over the entire study period (5-11 years, depending on the study site) were fatal. Higher baseline opioid dose was the strongest and most consistent predictor of opioid-involved overdose or opioid overdose-related death. Study exclusion criteria may have selected patients at lower risk of overdose, and substantial loss to follow-up (approximately 80%) also may have biased estimates.

The risk estimates from the studies described above may not be generalizable to all patients receiving opioid analgesics, such as those with exposures shorter or longer than the duration evaluated in the studies.

7 DRUG INTERACTIONS

Table 3 includes clinically significant drug interactions with NUCYNTA ER.

Table 3. Clinically Significant Drug Interactions with NUCYNTA ER
Alcohol
Clinical Impact: | Concomitant use of alcohol with NUCYNTA ER can result in an increase of tapentadol plasma levels and potentially fatal overdose of tapentadol.
Intervention: | Instruct patients not to consume alcoholic beverages or use prescription or non- prescription products containing alcohol while on NUCYNTA ER therapy [see Warnings and Precautions (5.3)].
Benzodiazepines and Other Central Nervous System (CNS) Depressants
Clinical Impact: | Due to additive pharmacologic effect, the concomitant use of benzodiazepines or other CNS depressants, including alcohol, can increase the risk of hypotension, respiratory depression, profound sedation, coma, and death [see Warnings and Precautions (5.3)].
Intervention: | Reserve concomitant prescribing of these drugs for use in patients for whom alternative treatment options are inadequate. Limit dosages and durations to the minimum required. Inform patients and caregivers of this potential interaction and educate them on the signs and symptoms of respiratory depression (including sedation). If concomitant use is warranted, consider recommending or prescribing an opioid overdose reversal agent [see Dosage and Administration (2.2), Warnings and Precautions (5.1, 5.2, 5.3)].
Examples: | Benzodiazepines and other sedatives/hypnotics, anxiolytics, tranquilizers, muscle relaxants, general anesthetics, antipsychotics, gabapentinoids (gabapentin or pregabalin), other opioids, alcohol
Serotonergic Drugs
Clinical Impact: | The concomitant use of opioids with other drugs that affect the serotonergic neurotransmitter system has resulted in serotonin syndrome [see Warnings and Precautions (5.7)].
Intervention: | If concomitant use is warranted, frequently evaluate the patient, particularly during treatment initiation and dose adjustment. Discontinue NUCYNTA ER if serotonin syndrome is suspected.
Examples: | Selective serotonin reuptake inhibitors (SSRIs), serotonin and norepinephrine reuptake inhibitors (SNRIs), tricyclic antidepressants (TCAs), triptans, 5-HT3 receptor antagonists, drugs that affect the serotonin neurotransmitter system (e.g., mirtazapine, trazodone, tramadol), certain muscle relaxants (i.e., cyclobenzaprine, metaxalone), monoamine oxidase (MAO) inhibitors (those intended to treat psychiatric disorders and also others, such as linezolid and intravenous methylene blue)
Monoamine Oxidase Inhibitors (MAOIs)
Clinical Impact: | MAOI interactions with opioids may manifest as serotonin syndrome or opioid toxicity (e.g., respiratory depression, coma) [see Warnings and Precautions (5.2)].
Intervention: | Do not use NUCYNTA ER in patients taking MAOIs or within 14 days of stopping such treatment
Examples: | phenelzine, tranylcypromine, linezolid
Mixed Agonist/Antagonist and Partial Agonist Opioid Analgesics
Clinical Impact: | May reduce the analgesic effect of NUCYNTA ER and/or precipitate withdrawal symptoms.
Intervention: | Avoid concomitant use.
Examples: | butorphanol, nalbuphine, pentazocine, buprenorphine
Muscle Relaxants
Clinical Impact: | Tapentadol may enhance the neuromuscular blocking action of skeletal muscle relaxants and produce an increased degree of respiratory depression.
Intervention: | Because respiratory depression may be greater than otherwise expected, decrease the dosage of NUCYNTA ER and/or the muscle relaxant as necessary. Due to the risk of respiratory depression with concomitant use of skeletal muscle relaxants and opioids, consider recommending or prescribing an opioid overdose reversal agent [see Dosage and Administration (2.2), Warnings and Precautions (5.2, 5.3)]
Examples: | cyclobenzaprine, metaxalone
Diuretics
Clinical Impact: | Opioids can reduce the efficacy of diuretics by inducing the release of antidiuretic hormone.
Intervention: | Evaluate patients for signs of diminished diuresis and/or effects on blood pressure and increase the dosage of the diuretic as needed.
Anticholinergic Drugs
Clinical Impact: | The concomitant use of anticholinergic drugs may increase risk of urinary retention and/or severe constipation, which may lead to paralytic ileus.
Intervention: | Evaluate patients for signs of urinary retention or reduced gastric motility when NUCYNTA ER is used concomitantly with anticholinergic drugs.

8 USE IN SPECIFIC POPULATIONS

8.1 Pregnancy

Risk Summary

Use of opioid analgesics for an extended period of time during pregnancy may cause neonatal opioid withdrawal syndrome [see Warnings and Precautions (5.4)]. Available data with NUCYNTA ER are insufficient to inform a drug- associated risk for major birth defects and miscarriage or adverse maternal outcomes. In animal reproduction studies, embryofetal mortality and structural malformations were observed with subcutaneous administration of tapentadol during organogenesis to rabbits and delays in skeletal maturation were observed in rats at exposures equivalent to and less than the maximum recommended human dose (MRHD), respectively. When administered to pregnant rats during organogenesis and through lactation, increased pup mortality was noted following oral tapentadol exposures to doses equivalent to the MRHD [see Data]. Based on animal data, advise pregnant women of the potential risk to a fetus.

The background risk of major birth defects and miscarriage for the indicated population is unknown. All pregnancies have a background risk of birth defect, loss, or other adverse reaction. In the U.S. general population, the estimated background risk of major birth defects and miscarriage in clinically recognized pregnancies is 2 to 4% and 15 to 20%, respectively.

Clinical Considerations

Fetal/neonatal adverse reactions

Use of opioid analgesics for an extended period of time during pregnancy for medical or nonmedical purposes can result in physical dependence in the neonate and neonatal opioid withdrawal syndrome shortly after birth. Neonatal opioid withdrawal syndrome presents as irritability, hyperactivity and abnormal sleep pattern, high pitched cry, tremor, vomiting, diarrhea, and failure to gain weight. The onset, duration, and severity of neonatal opioid withdrawal syndrome vary based on the specific opioid used, duration of use, timing and amount of last maternal use, and rate of elimination of the drug by the newborn. Observe newborns for symptoms of neonatal opioid withdrawal syndrome and manage accordingly [see Warnings and Precautions (5.4)].

Labor or Delivery

Opioids cross the placenta and may produce respiratory depression and psychophysiological effects in neonates. An opioid overdose reversal agent, such as naloxone or nalmefene must be available for reversal of opioid-induced respiratory depression in the neonate. NUCYNTA ER is not recommended for use in pregnant women during and immediately prior to labor, when use of shorter-acting analgesics or other analgesic techniques are more appropriate. Opioid analgesics, including NUCYNTA ER, can prolong labor through actions that temporarily reduce the strength, duration, and frequency of uterine contractions. However, this effect is not consistent and may be offset by an increased rate of cervical dilatation, which tends to shorten labor. Monitor neonates exposed to opioid analgesics during labor for signs of excess sedation and respiratory depression.

Data

Animal Data

Tapentadol HCl was evaluated for teratogenic effects in pregnant rats and rabbits following intravenous and subcutaneous exposure during the period of embryofetal organogenesis. When tapentadol was administered twice daily by the subcutaneous route in rats at dose levels of 10, 20, or 40 mg/kg/day [producing up to 1.36 times the plasma exposure at the maximum recommended human dose (MRHD) of 500 mg/day for NUCYNTA ER based on an area under the time-curve (AUC) comparison], no teratogenic effects were observed. Evidence of embryofetal toxicity included transient delays in skeletal maturation (i.e., reduced ossification) at the 40 mg/kg/day dose which was associated with significant maternal toxicity. Administration of tapentadol HCl in rabbits at doses of 4, 10, or 24 mg/kg/day by subcutaneous injection [producing 0.3, 0.8, and 2.5 times the plasma exposure at the MRHD based on an AUC comparison, respectively] revealed embryofetal toxicity at doses ≥10 mg/kg/day. Findings included reduced fetal viability, skeletal delays and other variations. In addition, there were multiple malformations including gastroschisis/thoracogastroschisis, amelia/phocomelia, and cleft palate at doses ≥10 mg/kg/day and above, and ablepharia, encephalopathy, and spina bifida at the high dose of 24 mg/kg/day.

Embryofetal toxicity, including malformations, may be secondary to the significant maternal toxicity observed in the study.

In a study of pre- and postnatal development in rats, oral administration of tapentadol at doses of 20, 50, 150, or 300 mg/kg/day to pregnant and lactating rats during the late gestation and early postnatal period [resulting in up to 2.28 times the plasma exposure at the MRHD on an AUC basis] did not influence physical or reflex development, the outcome of neurobehavioral tests or reproductive parameters. At maternal tapentadol doses ≥150 mg/kg/day, a dose-related increase in pup mortality was observed to postnatal Day 4. Treatment-related developmental delay was observed in the dead pups, including incomplete ossification. In addition, significant reductions in pup body weights and body weight gains at doses associated with maternal toxicity (150 mg/kg/day and above) were seen throughout lactation.

8.2 Lactation

Risk Summary

There is insufficient/limited information on the excretion of tapentadol in human or animal breast milk. Physicochemical and available pharmacodynamic/toxicological data on tapentadol point to excretion in breast milk and risk to the breastfeeding child cannot be excluded.

Because of the potential for serious adverse reactions including excess sedation and respiratory depression in a breastfed infant, advise patients that breast feeding is not recommended during treatment with NUCYNTA ER.

Clinical Considerations

Monitor infants exposed to NUCYNTA ER through breast milk for excess sedation and respiratory depression. Withdrawal symptoms can occur in breastfed infants when maternal administration of an opioid analgesic is stopped, or when breast-feeding is stopped.

8.3 Females and Males of Reproductive Potential

Infertility

Use of opioids for an extended period of time may cause reduced fertility in females and males of reproductive potential. It is not known whether these effects on fertility are reversible [see Adverse Reactions(6.2), Nonclinical Toxicology (13.1)].

8.4 Pediatric Use

The safety and efficacy of NUCYNTA ER in pediatric patients less than 18 years of age have not been established.

8.5 Geriatric Use

Of the total number of patients in Phase 2/3 double-blind, multiple-dose clinical studies of NUCYNTA ER, 28% (1023/3613) were 65 years and over, while 7% (245/3613) were 75 years and over. No overall differences in effectiveness or tolerability were observed between these patients and younger patients.

Elderly patients (aged 65 or older) may have increased sensitivity to tapentadol. In general, use caution when selecting a dosage for an elderly patient, usually starting at the low end of the dosing range, reflecting the greater frequency of decreased hepatic, renal, or cardiac function and of concomitant disease or other drug therapy [see Clinical Pharmacology (12.3)].

Respiratory depression is the chief risk for elderly patients treated with opioids and has occurred after large initial doses were administered to patients who were not opioid-tolerant or when opioids were co-administered with other agents that depress respiration. Titrate the dosage of NUCYNTA ER slowly in geriatric patients and frequently reevaluate the patient for signs of central nervous system and respiratory depression [see Warnings and Precautions (5.8)].

Tapentadol is known to be substantially excreted by the kidney, and the risk of adverse reactions to this drug may be greater in patients with impaired renal function. Because elderly patients are more likely to have decreased renal function, care should be taken in dose selection, and it may be useful to regularly evaluate renal function.

8.6 Hepatic Impairment

Use of NUCYNTA ER in patients with severe hepatic impairment (Child-Pugh Score 10-15) is not recommended. In patients with moderate hepatic impairment (Child-Pugh Score 7 to 9), dosage reduction of NUCYNTA ER is recommended [see Dosage and Administration (2.5)]. No dosage adjustment is recommended in patients with mild hepatic impairment (Child-Pugh Score 5 to 6) [see Warnings and Precautions (5.16), Clinical Pharmacology (12.3)].

8.7 Renal Impairment

Use of NUCYNTA ER in patients with severe renal impairment (creatinine clearance less than 30 mL/minute) is not recommended. No dosage adjustment is recommended in patients with mild or moderate renal impairment (creatinine clearance 30-90 mL/minute) [see Warnings and Precautions (5.17), Clinical Pharmacology (12.3)].

9 DRUG ABUSE AND DEPENDENCE

9.1 Controlled Substance

NUCYNTA ER contains tapentadol, a Schedule II controlled substance.

9.2 Abuse

NUCYNTA ER contains tapentadol, a substance with high potential for misuse and abuse, which can lead to the development of substance use disorder, including addiction [see Warnings and Precautions (5.1)].

Misuse is the intentional use, for therapeutic purposes, of a drug by an individual in a way other than prescribed by a healthcare provider or for whom it was not prescribed.

Abuse is the intentional, non-therapeutic use of a drug, even once, for its desirable psychological or physiological effects.

Drug addiction is a cluster of behavioral, cognitive, and physiological phenomena that may include a strong desire to take the drug, difficulties in controlling drug use (e.g., continuing drug use despite harmful consequences, giving a higher priority to drug use than other activities and obligations), and possible tolerance or physical dependence.

Misuse and abuse of NUCYNTA ER increases risk of overdose, which may lead to central nervous system and respiratory depression, hypotension, seizures, and death. The risk is increased with concurrent abuse of NUCYNTA ER with alcohol and/or other CNS depressants. Abuse of and addiction to opioids in some individuals may not be accompanied by concurrent tolerance and symptoms of physical dependence. In addition, abuse of opioids can occur in the absence of addiction.

All patients treated with opioids require careful and frequent reevaluation for signs of misuse, abuse, and addiction, because use of opioid analgesic products carries the risk of addiction even under appropriate medical use. Patients at high risk of NUCYNTA ER abuse include those with a history of prolonged use of any opioid, including products containing tapentadol, those with a history of drug or alcohol abuse, or those who use NUCYNTA ER in combination with other abused drugs.

"Drug-seeking" behavior is very common in persons with substance use disorders. Drug-seeking tactics include emergency calls or visits near the end of office hours, refusal to undergo appropriate examination, testing, or referral, repeated "loss" of prescriptions, tampering with prescriptions, and reluctance to provide prior medical records or contact information for other treating healthcare provider(s). "Doctor shopping" (visiting multiple prescribers to obtain additional prescriptions) is common among people who abuse drugs and people with substance use disorder. Preoccupation with achieving adequate pain relief can be appropriate behavior in a patient with inadequate pain control.

NUCYNTA ER, like other opioids, can be diverted for nonmedical use into illicit channels of distribution. Careful record-keeping of prescribing information, including quantity, frequency, and renewal requests, as required by state and federal law, is strongly advised.

Proper assessment of the patient, proper prescribing practices, periodic reevaluation of therapy, and proper dispensing and storage are appropriate measures that help to limit abuse of opioid drugs.

Risks Specific to Abuse of NUCYNTA ER

Abuse of NUCYNTA ER poses a risk of overdose and death. This risk is increased with the concurrent use of NUCYNTA ER with alcohol and/or other CNS depressants [see Warnings and Precautions (5.1, 5.3), Drug Interactions (7)].

NUCYNTA ER is approved for oral use only. With parenteral abuse, the inactive ingredients in NUCYNTA ER can result in local tissue necrosis, infection, pulmonary granulomas, increased risk of endocarditis and valvular heart injury, embolism and death.

Parenteral drug abuse is commonly associated with transmission of infectious diseases such as hepatitis and HIV.

9.3 Dependence

Both tolerance and physical dependence can develop during use of opioid therapy.

Tolerance is a physiological state characterized by a reduced response to a drug after repeated administration (i.e., a higher dose of a drug is required to produce the same effect that was once obtained at a lower dose).

Physical dependence is a state that develops as a result of a physiological adaptation in response to repeated drug use, manifested by withdrawal signs and symptoms after abrupt discontinuation or a significant dose reduction of a drug.

Withdrawal may be precipitated through the administration of drugs with opioid antagonist activity (e.g., naloxone, nalmefene), mixed agonist/antagonist analgesics (e.g., pentazocine, butorphanol, nalbuphine), or partial agonists (e.g., buprenorphine). Physical dependence may not occur to a clinically significant degree until after several days to weeks of continued use.

Do not rapidly reduce or abruptly discontinue NUCYNTA ER in a patient physically dependent on opioids. Rapid tapering of NUCYNTA ER in a patient physically dependent on opioids may lead to serious withdrawal symptoms, uncontrolled pain, and suicide. Rapid discontinuation has also been associated with attempts to find other sources of opioid analgesics, which may be confused with drug-seeking for abuse.

When discontinuing NUCYNTA ER, gradually taper the dosage using a patient-specific plan that considers the following: the dose of NUCYNTA ER the patient has been taking, the duration of treatment, and the physical and psychological attributes of the patient. To improve the likelihood of a successful taper and minimize withdrawal symptoms, it is important that the opioid tapering schedule is agreed upon by the patient. In patients taking opioids for an extended period of time at high doses, ensure that a multimodal approach to pain management, including mental health support (if needed), is in place prior to initiating an opioid analgesic taper [see Dosage and Administration (2.6), Warnings and Precautions (5.3)].

Infants born to mothers physically dependent on opioids will also be physically dependent and may exhibit respiratory difficulties and withdrawal signs [see Use in Specific Populations (8.1)].

10 OVERDOSAGE

Clinical Presentation

Acute overdosage with tapentadol can be manifested by respiratory depression, somnolence progressing to stupor or coma, skeletal muscle flaccidity, cold and clammy skin, constricted pupils, and, in some cases pulmonary edema, bradycardia, hypotension, hypoglycemia, partial or complete airway obstruction, atypical snoring and death. Marked mydriasis rather than miosis may be seen with hypoxia in overdose situations [see Clinical Pharmacology (12.2)]. Toxic leukoencephalopathy has been reported after opioid overdose and can present hours, days, or weeks after apparent recovery from the initial intoxication.

Treatment of Overdose

In case of overdose, priorities are the reestablishment of a patent and protected airway and institution of assisted or controlled ventilation, if needed. Employ other supportive measures (including oxygen, vasopressors) in the management of circulatory shock and pulmonary edema as indicated. Cardiac arrest or arrhythmias will require advanced life support measures.

For clinically significant respiratory or circulatory depression secondary to tapentadol overdose, administer an opioid overdose reversal agent such as naloxone or nalmefene.

Because the duration of reversal would be expected to be less than the duration of action of tapentadol in NUCYNTA ER, carefully monitor the patient until spontaneous respiration is reliably reestablished.

NUCYNTA ER will continue to release tapentadol and add to the tapentadol load for 24 to 48 hours or longer following ingestion, necessitating prolonged monitoring. If the response to an opioid overdose reversal agent is suboptimal or only brief in nature, additional reversal agent should be given as directed in the product's prescribing information.

In an individual physically dependent on opioids, administration of the recommended usual dosage of the opioid overdose reversal agent will precipitate an acute withdrawal syndrome. The severity of the withdrawal symptoms experienced will depend on the degree of physical dependence and the dose of the reversal agent administered. If a decision is made to treat serious respiratory depression in the physically dependent patient, administration of the reversal agent should be initiated with care and by titration with smaller than usual doses of the reversal agent.

11 DESCRIPTION

NUCYNTA ER (tapentadol) is an opioid agonist, supplied in extended-release film-coated tablets for oral administration, containing 58.24, 116.48, 174.72, 232.96, and 291.20 mg of tapentadol hydrochloride in each tablet strength, corresponding to 50, 100, 150, 200, and 250 mg of tapentadol free-base, respectively. The chemical name is 3-[(1R,2R)-3-(dimethylamino)-1-ethyl-2-methylpropyl]phenol monohydrochloride. The structural formula is:

The molecular weight of tapentadol HCl is 257.80, and the molecular formula is C14H23NO∙HCl. The n-octanol: water partition coefficient log P value is 2.89. The pKa values are 9.36 and 10.45. In addition to the active ingredient tapentadol HCl, tablets also contain the following inactive ingredients: alpha-tocopherol (vitamin E), hypromellose, polyethylene glycol, and polyethylene oxide. The film coating is comprised of polyvinyl alcohol, polyethylene glycol, talc, titanium dioxide, and the colorant FD&C Blue #2 aluminum lake is used for 100, 150, 200, and 250 mg strengths; and additionally, yellow iron oxide is used in 150 mg tablets.

Printing inks contain shellac glaze and propylene glycol for all strengths, and black iron oxide (50, 100, 150 and 200 mg tablets) or titanium dioxide (250 mg tablets).

12 CLINICAL PHARMACOLOGY

12.1 Mechanism of Action

Tapentadol is a centrally-acting synthetic analgesic. The exact mechanism of action is unknown. Although the clinical relevance is unclear, preclinical studies have shown that tapentadol is a mu-opioid receptor (MOR) agonist and a norepinephrine reuptake inhibitor (NRI). Analgesia in animal models is derived from both of these properties.

12.2 Pharmacodynamics

Effects on the Central Nervous System (CNS)

Tapentadol produces respiratory depression, by direct action on the brainstem respiratory centers. The respiratory depression involves a reduction in the responsiveness of the brain stem respiratory centers to both increases in carbon dioxide tension and electrical stimulation.

Tapentadol causes miosis, even in total darkness. Pinpoint pupils are a sign of opioid overdose but are not pathognomonic (e.g., pontine lesions of hemorrhagic or ischemic origin may produce similar findings).

Marked mydriasis rather than miosis may be seen with hypoxia in overdose situations.

Effects on the Gastrointestinal Tract and on Other Smooth Muscle

Tapentadol causes a reduction in motility and is associated with an increase in tone in the antrum of the stomach and duodenum. Digestion of food in the small intestine is delayed and propulsive contractions are decreased. Propulsive peristaltic waves in the colon are decreased, while tone is increased to the point of spasm, resulting in constipation. Other opioid induced effects may include a reduction in biliary and pancreatic secretions, spasm of the sphincter of Oddi, transient elevations in serum amylase, and opioid-induced esophageal dysfunction (OIED).

Effects on the Cardiovascular System

There was no effect of therapeutic and supratherapeutic doses of tapentadol on the QT interval. In a randomized, double-blind, placebo- and positive-controlled crossover study, healthy subjects were administered five consecutive immediate-release formulation doses of tapentadol 100 mg every 6 hours, tapentadol 150 mg every 6 hours, placebo and a single oral dose of moxifloxacin. Similarly, the immediate- release formulation tapentadol had no relevant effect on other ECG parameters (heart rate, PR interval, QRS duration, T-wave or U-wave morphology).

Tapentadol produces peripheral vasodilation which may result in orthostatic hypotension or syncope. Manifestations of histamine release and/or peripheral vasodilation may include pruritus, flushing, red eyes, sweating, and/or orthostatic hypotension.

Effects on the Endocrine System

Opioids inhibit the secretion of adrenocorticortropic hormone (ACTH), cortisol, and luteinizing hormone (LH) in humans [see Adverse Reactions (6.2)]. They also stimulate prolactin, growth hormone (GH) secretion, and pancreatic secretion of insulin and glucagon.

Use of opioids for an extended period of time may influence the hypothalamic-pituitary-gonadal axis, leading to androgen deficiency that may manifest as low libido, impotence, erectile dysfunction, amenorrhea, or infertility. The causal role of opioids in the clinical syndrome of hypogonadism is unknown because the various medical, physical, lifestyle, and psychological stressors that may influence gonadal hormone levels have not been adequately controlled for in studies conducted to date [see Adverse Reactions (6.2)].

Effects on the ImmuneSystem

Opioids have been shown to have a variety of effects on components of the immune system in in vitro and animal models. The clinical significance of these findings is unknown. Overall, the effects of opioids appear to be modestly immunosuppressive.

Concentration-Efficacy Relationships

The minimum effective analgesic concentration will vary widely among patients, especially among patients who have been previously treated with opioid agonists. The minimum effective analgesic concentration of tapentadol for any individual patient may increase over time due to an increase in pain, development of a new pain syndrome, and/or potential development of analgesic tolerance [see Dosage and Administration (2.1, 2.4)].

Concentration-Adverse Experience Relationships

There is a relationship between increasing tapentadol plasma concentration and increasing frequency of dose- related adverse reactions such as nausea, vomiting, CNS effects, and respiratory depression. In opioid- tolerant patients, the situation may be altered by the development of tolerance to opioid-related adverse reactions [see Dosage and Administration (2.1, 2.3, 2.4)].

12.3 Pharmacokinetics

Absorption

The mean absolute bioavailability after single-dose administration (fasting) of NUCYNTA ER is approximately 32% due to extensive first-pass metabolism. Maximum serum concentrations of tapentadol are observed between 3 and 6 hours after administration of NUCYNTA ER. Dose proportional increases for AUC have been observed after administration of NUCYNTA ER over the therapeutic dose range.

Steady-state exposure of tapentadol is attained after the third dose (i.e., 24 hours after first twice daily multiple dose administration). Following dosing with 250 mg every 12 hours, minimal accumulation was observed.

Food Effect

The AUC and Cmax increased by 6% and 17%, respectively, when NUCYNTA ER tablet was administered after a high-fat, high-calorie breakfast. NUCYNTA ER may be given with or without food.

Distribution

Tapentadol is widely distributed throughout the body. Following intravenous administration, the volume of distribution (Vz) for tapentadol is 540 +/- 98 L. The plasma protein binding is low and amounts to approximately 20%.

Elimination

Metabolism

In humans, about 97% of the parent compound is metabolized. Tapentadol is mainly metabolized via Phase 2 pathways, and only a small amount is metabolized by Phase 1 oxidative pathways. The major pathway of tapentadol metabolism is conjugation with glucuronic acid to produce glucuronides. After oral administration approximately 70% (55% O-glucuronide and 15% sulfate of tapentadol) of the dose is excreted in urine in the conjugated form. A total of 3% of drug was excreted in urine as unchanged drug. Tapentadol is additionally metabolized to N-desmethyl tapentadol (13%) by CYP2C9 and CYP2C19 and to hydroxy tapentadol (2%) by CYP2D6, which are further metabolized by conjugation. Therefore, drug metabolism mediated by cytochrome P450 system is of less importance than phase 2 conjugation.

None of the metabolites contribute to the analgesic activity.

Excretion

Tapentadol and its metabolites are excreted almost exclusively (99%) via the kidneys. The terminal half-life is on average 5 hours after oral administration. The total clearance of tapentadol is 1603 +/-227 mL/min.

Specific Populations

Age: Geriatric Population

The mean exposure (AUC) to tapentadol was similar in elderly subjects compared to young adults, with a 16% lower mean Cmax observed in the elderly subject group compared to young adult subjects.

Hepatic Impairment

Administration of tapentadol resulted in higher exposures and serum levels to tapentadol in subjects with impaired hepatic function compared to subjects with normal hepatic function. The ratio of tapentadol pharmacokinetic parameters for the mild hepatic impairment group (Child-Pugh Score 5 to 6) and moderate hepatic impairment group (Child-Pugh Score 7 to 9) in comparison to the normal hepatic function group were 1.7 and 4.2, respectively, for AUC; 1.4 and 2.5, respectively, for Cmax; and 1.2 and 1.4, respectively, for t1/2. The rate of formation of tapentadol-O-glucuronide was lower in subjects with increased liver impairment.

Renal Impairment

AUC and Cmax of tapentadol were comparable in subjects with varying degrees of renal function (from normal to severely impaired). In contrast, increasing exposure (AUC) to tapentadol-O-glucuronide was observed with increasing degree of renal impairment. In subjects with mild (CLCR= 50 to <80 mL/min), moderate (CLCR= 30 to<50 mL/min), and severe (CLCR= <30 mL/min) renal impairment, the AUC of tapentadol-O-glucuronide was 1.5-, 2.5-, and 5.5-fold higher compared with normal renal function, respectively.

Drug Interaction Studies

Tapentadol is mainly metabolized by Phase 2 glucuronidation, a high capacity/low affinity system; therefore, clinically relevant interactions caused by Phase 2 metabolism are unlikely to occur. Naproxen and probenecid increased the AUC of tapentadol by 17% and 57%, respectively. These changes are not considered clinically relevant and no change in dose is required.

No changes in the pharmacokinetic parameters of tapentadol were observed when acetaminophen and acetylsalicylic acid were given concomitantly.

In vitro studies did not reveal any potential of tapentadol to either inhibit or induce cytochrome P450 enzymes. Only a minor amount of tapentadol is metabolized via the oxidative pathway. Thus, clinically relevant interactions mediated by the cytochrome P450 system are unlikely to occur.

The pharmacokinetics of tapentadol were not affected when gastric pH or gastrointestinal motility were increased by omeprazole and metoclopramide, respectively.

Plasma protein binding of tapentadol is low (approximately 20%). Therefore, the likelihood of pharmacokinetic drug-drug interactions by displacement from the protein binding site is low.

Alcohol

NUCYNTA ER may be expected to have additive effects when used in conjunction with alcohol, other opioids, or illicit drugs that cause central nervous system depression, because respiratory depression, hypotension, hypertension, and profound sedation, coma or death may result [see Warnings and Precautions (5.5)].

An in vivo study examined the effect of alcohol (240 mL of 40%) on the bioavailability of a single dose of 100 mg and 250 mg of NUCYNTA ER tablet in healthy, fasted volunteers. After co-administration of a 100 mg NUCYNTA ER tablet and alcohol, the mean Cmax value increased by 48% compared to control with a range of 0.99-fold to 4.38-fold. The mean tapentadol AUClast and AUCinf were increased by 17%; the Tmax and t½ were unchanged. After co-administration of a 250 mg NUCYNTA ER tablet and alcohol, the mean Cmax value increased by 28% compared to control with a range of 0.90-fold to 2.67-fold. The mean tapentadol AUClast and AUCinf were increased by 16%; the Tmax and t½ were unchanged.

13 NONCLINICAL TOXICOLOGY

13.1 Carcinogenesis, Mutagenesis, Impairment of Fertility

Carcinogenesis

In mice, tapentadol HCl was administered by oral gavage at dosages of 50, 100 and 200 mg/kg/day for 2 years (up to 0.34 times in the male mice and 0.25 times in the female mice the plasma exposure at the maximum recommended human dose [MRHD] for NUCYNTA ER on an area under the time-curve [AUC] basis). No increase in tumor incidence was observed at any dose level.

In rats, tapentadol HCl was administered in diet at dosages of 10, 50, 125 and 250 mg/kg/day for two years (up to 0.20 times in the male rats and 0.75 times in the female rats the plasma exposure at the MRHD on an AUC basis). No increase in tumor incidence was observed at any dose level.

Mutagenesis

Tapentadol did not induce gene mutations in bacteria but was clastogenic with metabolic activation in a chromosomal aberration test in V79 cells. The test was repeated and was negative in the presence and absence of metabolic activation. The one positive result for tapentadol was not confirmed in vivo in rats, using the two endpoints of chromosomal aberration and unscheduled DNA synthesis, when tested up to the maximum tolerated dose.

Impairment of Fertility

Tapentadol HCl was administered intravenously to male or female rats at dosages of 3, 6, or 12 mg/kg/day (representing exposures of up to approximately 0.56 times in the male rats and 0.50 times in the female rats the exposure at the MRHD on an AUC basis, based on extrapolation from toxicokinetic analyses in a separate 4-week intravenous study in rats).

Tapentadol did not alter fertility at any dose level. Maternal toxicity and adverse effects on embryonic development, including decreased number of implantations, decreased numbers of live conceptuses, and increased pre- and post-implantation losses occurred at dosages ≥6 mg/kg/day.

13.2 Animal Toxicology and/or Pharmacology

In toxicological studies with tapentadol, the most common systemic effects of tapentadol were related to the mu-opioid receptor agonist and norepinephrine reuptake inhibition pharmacodynamic properties of the compound. Transient, dose-dependent and predominantly CNS-related findings were observed, including impaired respiratory function and convulsions, the latter occurring in the dog at plasma levels (Cmax), which are in the range associated with the maximum recommended human dose (MRHD).

14 CLINICAL STUDIES

14.1 Clinical Trials Summary

The efficacy of NUCYNTA ER was studied in five studies in patients with chronic pain and DPN. Efficacy was demonstrated in one randomized, double-blind, placebo- and active-controlled study in patients with chronic low back pain (LBP), and two randomized, double-blind, placebo-controlled studies in patients with pain related to diabetic peripheral neuropathy (DPN-1 and DPN-2).

14.2 Moderate to Severe Chronic Low Back Pain

In the LBP study, patients 18 years of age or older with chronic low back pain and a baseline pain score of ≥5 on an 11-point numerical rating scale (NRS), ranging from 0 to 10 were enrolled and randomized to 1 of 3 treatments: NUCYNTA ER, active-control (an extended-release Schedule II opioid analgesic), or placebo.

Patients randomized to NUCYNTA ER initiated therapy with a dose of 50 mg twice daily for three days. After three days, the dose was increased to 100 mg twice daily. Subsequent titration was allowed over a 3-week titration period to a dose up to 250 mg twice daily, followed by a 12-week maintenance period. There were 981 patients randomized. The mean age of the study population was 50 (range 18 to 89) years; the mean baseline pain intensity score was 8 (SD 1). Approximately half of the patients had not taken opioids during the three months prior to the screening visit.

The number of patients completing the study was 51% in the placebo group, 54% in the NUCYNTA ER group and 43% in the active-control group. Lack of efficacy was the most common reason for discontinuation among placebo-treated patients (21%), whereas adverse events were the most common reason for discontinuation among the active treatment groups (17% and 32% for NUCYNTA ER and active-control, respectively).

After 15 weeks of treatment, patients taking NUCYNTA ER had a significantly greater pain reduction compared to placebo. The proportion of patients with various degrees of improvement is shown in Figure 1. The figure is cumulative, such that patients, whose change from baseline is, for example 50%, are also included at every level of improvement below 50%. Patients who did not complete the study were assigned 0% improvement.

Figure 1. Percentage of Patients Achieving Various Levels of Improvement in Pain Intensity - Study LBP [The last week of Study LBP was Week 15.]

14.3 Neuropathic Pain Associated with Diabetic Peripheral Neuropathy

In the two DPN studies, patients 18 years of age or older with pain due to diabetic peripheral neuropathy and a pain score of ≥5 on an 11-point numerical rating scale (NRS) ranging from 0 (no pain) to 10 (worst possible pain) were enrolled. Following an open-label treatment period in which NUCYNTA ER was administered to all patients for three weeks and titrated to an individually stable dose, patients who had tolerated the drug and demonstrated at least a 1-point improvement in pain intensity on the NRS at the end of the open-label titration period were randomized to either continue the NUCYNTA ER dose (100 mg to 250 mg twice a day) reached during the open-label titration period, or receive placebo for 12 weeks of maintenance treatment. During the first 4 days of the double-blind maintenance period patients were permitted to take tapentadol ER 25 mg up to two times a day as additional medication. After the first 4 days, patients were allowed to take tapentadol ER 25 mg once daily as needed for pain, in addition to the patient's assigned study drug. Patients recorded their pain in a diary twice daily.

Study DPN-1: A total of 591 patients entered open-label treatment and 389 patients met the criteria for randomization into the double-blind treatment period. The mean age of the randomized population was 60 (range 29 to 87) years; approximately two-thirds of the patients had not taken opioids during the three months prior to the screening visit.

During the titration period, 34% of patients discontinued open-label NUCYNTA ER. The most common reasons for discontinuation in the double-blind treatment period were lack of efficacy in the placebo group (14%) and adverse events in the NUCYNTA ER group (15%).

After 12 weeks of treatment, NUCYNTA ER provided a significantly greater reduction in pain intensity from baseline to the end of the 12-week double-blind period compared to placebo. Figure 2 displays the proportion of randomized patients achieving various degrees of improvement in pain intensity from the start of the open-label titration period to the last week of the randomized withdrawal period. The figure is cumulative, such that patients, whose change from baseline is, for example 50%, are also included at every level of improvement below 50%. Patients who did not complete the study were assigned 0% improvement.

Figure 2. Percentage of Patients Achieving Various Levels of Improvement in Pain Intensity - PN-1ACCE

Study DPN-2: A total of 459 patients entered open-label treatment and 320 patients met the criteria for randomization into the double-blind treatment period. The mean age of the randomized population was 59 (range 28 to 83) years; approximately two-thirds of the patients had not taken opioids during the three months prior to the screening visit.

During the titration period, 22% of patients discontinued open-label NUCYNTA ER and 6% of patients were not subsequently randomized because they failed to have at least 1-point improvement in pain intensity. The most common reason for discontinuation in the double-blind treatment period was adverse events in both the placebo group (9%) and the NUCYNTA ER group (14%).

After 12 weeks of treatment, NUCYNTA ER provided a significantly greater reduction in pain intensity from baseline to the end of the 12-week double-blind period compared to placebo. Figure 3 displays the proportion of randomized patients achieving various degrees of improvement in pain intensity from the start of the open-label titration period to the last week of the randomized withdrawal period. The figure is cumulative, such that patients, whose change from baseline is, for example 50%, are also included at every level of improvement below 50%. Patients who did not complete the study were assigned 0% improvement.

Figure 3. Percentage of Patients Achieving Various Levels of Improvement in Pain Intensity - DPN-2

16 HOW SUPPLIED/STORAGE AND HANDLING

NUCYNTA ER tablets are available in the following strengths and packages:

50 mg extended-release tablets are white oblong-shaped with a black print "OMJ 50" on one side and are available in bottles of 60 with child-resistant closure (NDC 24510-058-60) and unit dose blister packs of 100 (10 blister strips of 10 tablets each), for hospital use only (NDC 24510-058-01).

100 mg extended-release tablets are light-blue oblong-shaped with a black print "OMJ 100" on one side and are available in bottles of 60 with child-resistant closure (NDC 24510-116-60) and unit dose blister packs of 100 (10 blister strips of 10 tablets each), for hospital use only (NDC 24510-116-01).

150 mg extended-release tablets are blue-green oblong-shaped with a black print "OMJ 150" on one side and are available in bottles of 60 with child-resistant closure (NDC 24510-174-60) and unit dose blister packs of 100 (10 blister strips of 10 tablets each), for hospital use only (NDC 24510-174-01).

200 mg extended-release tablets are blue oblong-shaped with a depression in the middle running lengthwise on each side and with a black print "OMJ 200" on one side, and are available in bottles of 60 with child- resistant closure (NDC 24510-232-60) and unit dose blister packs of 100 (10 blister strips of 10 tablets each), for hospital use only (NDC 24510-232-01).

250 mg extended-release tablets are dark blue oblong-shaped with a depression in the middle running lengthwise on each side and with a white print "OMJ 250" on one side, and are available in bottles of 60 with child-resistant closure (NDC 24510-291-60) and unit dose blister packs of 100 (10 blister strips of 10 tablets each), for hospital use only (NDC 24510-291-01).

Storage and Handling

Store at 20°C - 25°C (68°F - 77°F); excursions permitted to 15° C - 30°C (59° F - 86°F) [see USP Controlled Room Temperature].

Protect from moisture.

Store NUCYNTA ER securely and dispose of properly.

17 PATIENT COUNSELING INFORMATION

Advise the patient to read the FDA-approved patient labeling (Medication Guide).

Storage and Disposal

Because of the risks associated with accidental ingestion, misuse, and abuse, advise patients to store NUCYNTA ER securely, out of sight and reach of children, and in a location not accessible by others, including visitors to the home. Inform patients that leaving NUCYNTA ER unsecured can pose a deadly risk to others in the home [see Warnings and Precautions (5.1, 5.2), Drug Abuse and Dependence (9.2)].

Advise patients and caregivers that when medicines are no longer needed, they should be disposed of promptly. Expired, unwanted, or unused NUCYNTA ER Tablets should be disposed of by flushing the unused medication down the toilet if a drug take-back option is not readily available. Inform patients that they can visit www.fda.gov/drugdisposal for a complete list of medicines recommended for disposal by flushing, as well as additional information on disposal of unused medicines.

Addiction, Abuse, and Misuse

Inform patients that the use of NUCYNTA ER, even when taken as recommended, can result in addiction, abuse, and misuse, which can lead to overdose or death [see Warnings and Precautions (5.1)]. Instruct patients not to share NUCYNTA ER with others and to take steps to protect NUCYNTA ER from theft or misuse.

Life-threatening Respiratory Depression

Inform patients of the risk of life-threatening respiratory depression, including information that the risk is greatest when starting NUCYNTA ER or when the dosage is increased, and that it can occur even at recommended dosages.

Educate patients and caregivers on how to recognize respiratory depression and emphasize the importance of calling 911 or getting emergency medical help right away in the event of a known or suspected overdose [see Warnings and Precautions (5.2)].

Accidental Ingestion

Inform patients that accidental ingestion, especially by children, may result in respiratory depression or death [see Warnings and Precautions (5.2)].

Interactions with Benzodiazepines and other CNS Depressants

Instruct patients not to consume alcoholic beverages, as well as prescription and over-the-counter products that contain alcohol, during treatment with NUCYNTA ER. The co-ingestion of alcohol with NUCYNTA ER may result in increased plasma levels and a potentially fatal overdose of oxymorphone [see Warnings and Precautions (5.3)].

Inform patients and caregivers that potentially fatal additive effects may occur if NUCYNTA ER is used with benzodiazepines or other CNS depressants, including alcohol (e.g., non-benzodiazepine sedative/hypnotics, anxiolytics, tranquilizers, muscle relaxants, general anesthetics, antipsychotics, gabapentinoids [gabapentin or pregabalin], and other opioids), and not to use these concomitantly unless supervised by a health care provider [see Warnings and Precautions (5.3), Drug Interactions (7)].

Patient Access to an Opioid Overdose Reversal Agent for the Emergency Treatment of Opioid Overdose

Inform patients and caregivers about opioid overdose reversal agents (e.g., naloxone, nalmefene). Discuss the importance of having access to an opioid overdose reversal agent, especially if the patient has risk factors for overdose (e.g., concomitant use of CNS depressants, a history of opioid use disorder, or prior opioid overdose) or if there are household members (including children) or other close contacts at risk for accidental ingestion or opioid overdose.

Discuss with the patient the options for obtaining an opioid overdose reversal agent (e.g., prescription, over-the-counter, or as part of a community-based program) [see Dosage and Administration (2.2), Warnings and Precautions (5.2)].

Educate patients and caregivers on how to recognize the signs and symptoms of an overdose.

Explain to patients and caregivers that effects of opioid overdose reversal agent like naloxone and nalmefene are temporary, and that they must call 911 or get emergency medical help right away in all cases of known or suspected opioid overdose, even if an opioid overdose reversal agent is administered [see Overdosage (10)].

Advise patients and caregivers:

- how to treat with the overdose reversal agent in the event of an opioid overdose.
- to tell family and friends about their opioid overdose reversal agent, and to keep it in a place where family and friends can access it in an emergency.
- to read the Patient Information (or other educational material) that will come with their opioid overdose reversal agent. Emphasize the importance of doing this before an opioid emergency happens, so the patient and caregiver will know what to do.

Hyperalgesia and Allodynia

Inform patients and caregivers not to increase opioid dosage without first consulting a clinician. Advise patients to seek medical attention if they experience symptoms of hyperalgesia, including worsening pain, increased sensitivity to pain, or new pain [see Warnings and Precautions (5.6); Adverse Reactions (6.2)].

Serotonin Syndrome

Inform patients that opioids could cause a rare but potentially life-threatening condition called serotonin syndrome resulting from concomitant administration of serotonergic drugs. Warn patients of the symptoms of serotonin syndrome and to seek medical attention right away if symptoms develop. Instruct patients to inform their healthcare providers if they are taking, or plan to take serotonergic medications [see Warnings and Precautions (5.7), Drug Interactions (7)].

Seizures

Inform patients that NUCYNTA ER could cause seizures if they are at risk for seizures or have epilepsy. Patients should be advised to stop taking NUCYNTA ER if they have a seizure while taking NUCYNTA ER and call their healthcare provider right away [see Warnings and Precautions (5.13)].

MAOI Interaction

Inform patients not to take NUCYNTA ER while using any drugs that inhibit monoamine oxidase. Patients should not start MAOIs while taking NUCYNTA ER [see Drug Interactions (7)].

Important Administration Instructions

Instruct patients how to properly take NUCYNTA ER, including the following:

- Using NUCYNTA ER exactly as prescribed to reduce the risk of life-threatening adverse reactions (e.g., respiratory depression) [see Dosage and Administration (2)]
- Swallowing NUCYNTA ER tablets whole [see Dosage and Administration (2.1)]
- To take each tablet with enough water to ensure complete swallowing immediately after placing in mouth [see Dosage and Administration (2.1)]
- Not cutting, crushing, chewing, or dissolving the tablets [see Dosage and Administration (2.1)]

Important Discontinuation Instructions

In order to avoid developing withdrawal symptoms, instruct patients not to discontinue NUCYNTA ER without first discussing a tapering plan with the prescriber [see Dosage and Administration (2.6)]

Driving or Operating Heavy Machinery

Inform patients that NUCYNTA ER may impair the ability to perform potentially hazardous activities such as driving a car or operating heavy machinery. Advise patients not to perform such tasks until they know how they will react to the medication [see Warnings and Precautions (5.15)].

Constipation

Advise patients of the potential for severe constipation, including management instructions and when to seek medical attention.

Adrenal Insufficiency

Inform patients that NUCYNTA ER could cause adrenal insufficiency, a potentially life- threatening condition. Adrenal insufficiency may present with non-specific symptoms and signs such as nausea, vomiting, anorexia, fatigue, weakness, dizziness, and low blood pressure. Advise patients to seek medical attention if they experience a constellation of these symptoms [see Warnings and Precautions (5.9)].

Hypotension

Inform patients that NUCYNTA ER may cause orthostatic hypotension and syncope. Instruct patients how to recognize symptoms of low blood pressure and how to reduce the risk of serious consequences should hypotension occur (e.g., sit or lie down, carefully rise from a sitting or lying position) [see Warnings and Precautions (5.10)].

Anaphylaxis

Inform patients that anaphylaxis has been reported with ingredients contained in NUCYNTA ER. Advise patients how to recognize such a reaction and when to seek medical attention [see Contraindications (4), Adverse Reactions (6.2)].

Pregnancy

Neonatal Opioid Withdrawal Syndrome

Inform female patients of reproductive potential that use of NUCYNTA ER for an extended period of time during pregnancy can result in neonatal opioid withdrawal syndrome, which may be life-threatening if not recognized and treated [see Warnings and Precautions (5.4), Use in Specific Populations (8.1)].

Embryo-Fetal Toxicity

Advise female patients that NUCYNTA ER can cause fetal harm and to inform the prescriber if they are pregnant or plan to become pregnant [see Use in Specific Populations (8.1)].

Lactation

Advise patients that breastfeeding is not recommended during treatment with NUCYNTA ER [see Use in Specific Populations (8.2)]

Infertility

Inform patients that use of opioids for an extended period of time may cause reduced fertility. It is not known whether these effects on fertility are reversible [see Use in Specific Populations (8.3)].

Distributed by: Collegium Pharmaceutical, Inc., Stoughton, MA 02072

U.S. Patent Nos. 6071970, 7994364, 8075872, 8114383, 8309060, 8420056, 8536130, and RE39593.

NUCX-011-C.11

Revised: Month 2026

Medication Guide
NUCYNTA® ER (new-SINN-tah E-R) (tapentadol) extended-release oral tablets, CII

NUCYNTA ER is:

- A strong prescription pain medicine that contains an opioid (narcotic) that is used to manage severe and persistent pain in adults that requires an extended treatment period with a daily opioid pain medicine, when other pain medicines do not treat your pain well enough or you cannot tolerate them.
- Also used in adults to manage severe and persistent pain from damaged nerves (neuropathic pain) that happens with diabetes, and that requires an extended treatment period with a daily opioid pain medicine, when other pain medicines do not treat your pain well enough or you cannot tolerate them.
- A long-acting (extended-release) opioid pain medicine that can put you at risk for overdose and death. Even if you take your dose correctly as prescribed you are at risk for opioid addiction, abuse, and misuse that can lead to death.
- Not to be taken on an "as needed" basis.

Important information about NUCYNTA ER:

- Get emergency help or call 911 right away if you take too much NUCYNTA ER (overdose). When you first start taking NUCYNTA ER, when your dose is changed, or if you take too much (overdose), serious or life-threatening breathing problems that can lead to death may occur. Ask your healthcare provider about medicines like naloxone or nalmefene that can be used in an emergency to reverse an opioid overdose.
- Taking NUCYNTA ER with other opioid medicines, benzodiazepines, gabapentinoids (gabapentin or pregabalin), alcohol, or other central nervous system depressants (including street drugs) can cause severe drowsiness, decreased awareness, breathing problems, coma, and death.
- Never give anyone else your NUCYNTA ER. They could die from taking it. Selling or giving away NUCYNTA ER is against the law.
- Store NUCYNTA ER securely, out of sight and reach of children, and in a location not accessible by others, including visitors to the home.

Do not take NUCYNTA ER if you have:

- severe asthma, trouble breathing, or other lung problems.
- a bowel blockage or have narrowing of the stomach or intestines.

Before taking NUCYNTA ER, tell your healthcare provider if you have a history of:

- head injury, seizures
- problems urinating

- liver, kidney, thyroid problems
- pancreas or gallbladder problems

- abuse of street or prescription drugs, alcohol addiction, opioid overdose, or mental health problems.

Tell your healthcare provider if you are:

- noticing your pain getting worse. If your pain gets worse after you take NUCYNTA ER, do not take more of NUCYNTA ER without first talking to your healthcare provider. Talk to your healthcare provider if the pain that you have increases, if you feel more sensitive to pain, or if you have new pain after taking NUCYNTA ER.
- pregnant or planning to become pregnant. Use of NUCYNTA ER for an extended period of time during pregnancy can cause withdrawal symptoms in your newborn baby that could be life-threatening if not recognized and treated.
- breastfeeding. Not recommended during treatment with NUCYNTA ER. It may harm your baby.
- living in a household where there are small children or someone who has abused street or prescription drugs.
- taking prescription or over-the-counter medicines, vitamins, or herbal supplements. Taking NUCYNTA ER with certain other medicines can cause serious side effects.

When taking NUCYNTA ER:

- Do not change your dose. Take NUCYNTA ER exactly as prescribed by your healthcare provider. Use the lowest effective dose for the shortest time needed.
- Take your prescribed dose every 12 hours, at the same time every day. Do not take more than your prescribed dose in 24 hours. If you miss a dose, take your next dose at your usualtime.
- Swallow NUCYNTA ER whole. Do not cut, break, chew, crush, dissolve, snort, or inject NUCYNTA ER because this may cause you to overdose and die.
- Call your healthcare provider if the dose you are taking does not control your pain.
- Do not stop taking NUCYNTA ER without talking to your healthcare provider.
- Dispose of expired, unwanted, or unused NUCYNTA ER by promptly flushing down the toilet, if a drug take-back option is not readily available. Visit www.fda.gov/drugdisposal for additional information on disposal of unused medicines.

While taking NUCYNTA ER DO NOT:

- Drive or operate heavy machinery until you know how NUCYNTA ER affects you. NUCYNTA ER can make you sleepy, dizzy, or lightheaded.
- Drink alcohol or use prescription or over-the-counter medicines containing alcohol. Using products containing alcohol during treatment with NUCYNTA ER may cause you to overdose and die.

The possible side effects of NUCYNTA ER are:

- constipation, nausea, sleepiness, vomiting, tiredness, headache, dizziness, abdominal pain. Call your healthcare provider if you have any of these symptoms and they are severe.

Get emergency medical help or call 911 right away if you have:

- trouble breathing, shortness of breath, fast heartbeat, chest pain, swelling of your face, tongue, or throat, extreme drowsiness, light-headedness when changing positions, feeling faint, agitation, high body temperature, trouble walking, stiff muscles, or mental changes such as confusion.
- agitation, hallucinations, coma, feeling overheated, or heavy sweating.

These are not all the possible side effects of NUCYNTA ER. Call your healthcare provider for medical advice about side effects. You may report side effects to FDA at 1-800-FDA-1088. For more information go to dailymed.nlm.nih.gov
Distributed by: Collegium Pharmaceutical, Inc., 100 Technology Center Drive Suite 300, Stoughton, MA, 02072, www.collegiumpharma.com or call 1-855-331-5615.

This Medication Guide has been approved by the U.S. Food and Drug Administration

Revised: December 2025

NUCX-012-C.5

PRINCIPAL DISPLAY PANEL - 50 mg Tablet Bottle Label

NDC 24510-058-60
60 Tablets

Nucynta® ER

(tapentadol)
Extended Release Tablets

50 mg
CII
Rx only

Each tablet contains 50 mg tapentadol.

Swallow tablets whole. Do not chew, crush
or dissolve.

Caution: Federal law prohibits the transfer of this drug
to any person other than the patient for whom, it was
prescribed.

Dispense the accompanying Medication Guide
to each patient.

PRINCIPAL DISPLAY PANEL - 100 mg Tablet Bottle Label

NDC 24510-116-60
60 Tablets

Nucynta® ER

(tapentadol)
Extended Release Tablets

100 mg
CII
Rx only

Each tablet contains 100 mg tapentadol.

Swallow tablets whole. Do not chew, crush
or dissolve.

Caution: Federal law prohibits the transfer of this drug
to any person other than the patient for whom, it was
prescribed.

Dispense the accompanying Medication Guide
to each patient.

PRINCIPAL DISPLAY PANEL - 150 mg Tablet Bottle Label

NDC 24510-174-60
60 Tablets

Nucynta® ER

(tapentadol)
Extended Release Tablets

150 mg
CII
Rx only

Each tablet contains 150 mg tapentadol.

Swallow tablets whole. Do not chew, crush
or dissolve.

Caution: Federal law prohibits the transfer of this drug
to any person other than the patient for whom, it was
prescribed.

Dispense the accompanying Medication Guide
to each patient.

PRINCIPAL DISPLAY PANEL - 200 mg Tablet Bottle Label

NDC 24510-232-60
60 Tablets

Nucynta® ER

(tapentadol)
Extended Release Tablets

200 mg
CII
Rx only

Each tablet contains 200 mg tapentadol.

Swallow tablets whole. Do not chew, crush
or dissolve.

Caution: Federal law prohibits the transfer of this drug
to any person other than the patient for whom, it was
prescribed.

Dispense the accompanying Medication Guide
to each patient.

PRINCIPAL DISPLAY PANEL - 250 mg Tablet Bottle Label

NDC 24510-291-60
60 Tablets

Nucynta® ER

(tapentadol)
Extended Release Tablets

250 mg
CII
Rx only

Each tablet contains 250 mg tapentadol.

Swallow tablets whole. Do not chew, crush
or dissolve.

Caution: Federal law prohibits the transfer of this drug
to any person other than the patient for whom, it was
prescribed.

Dispense the accompanying Medication Guide
to each patient.